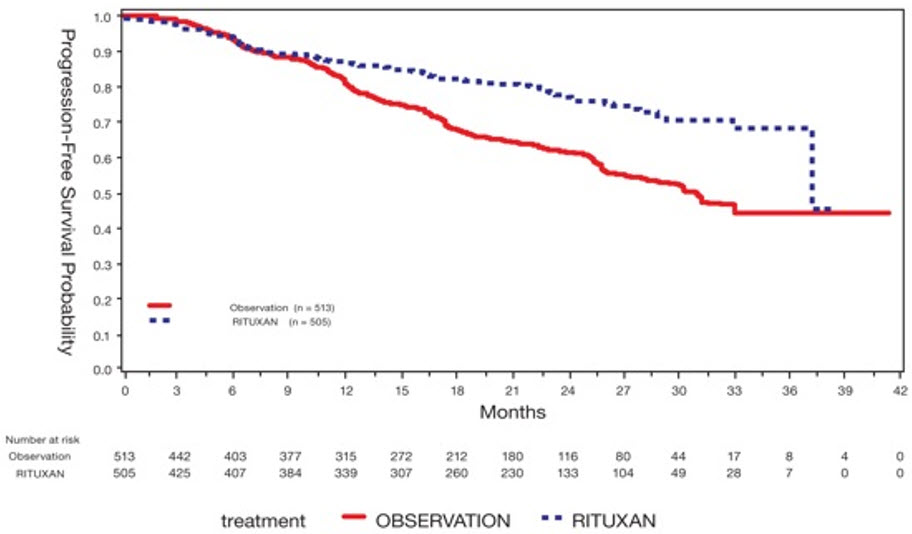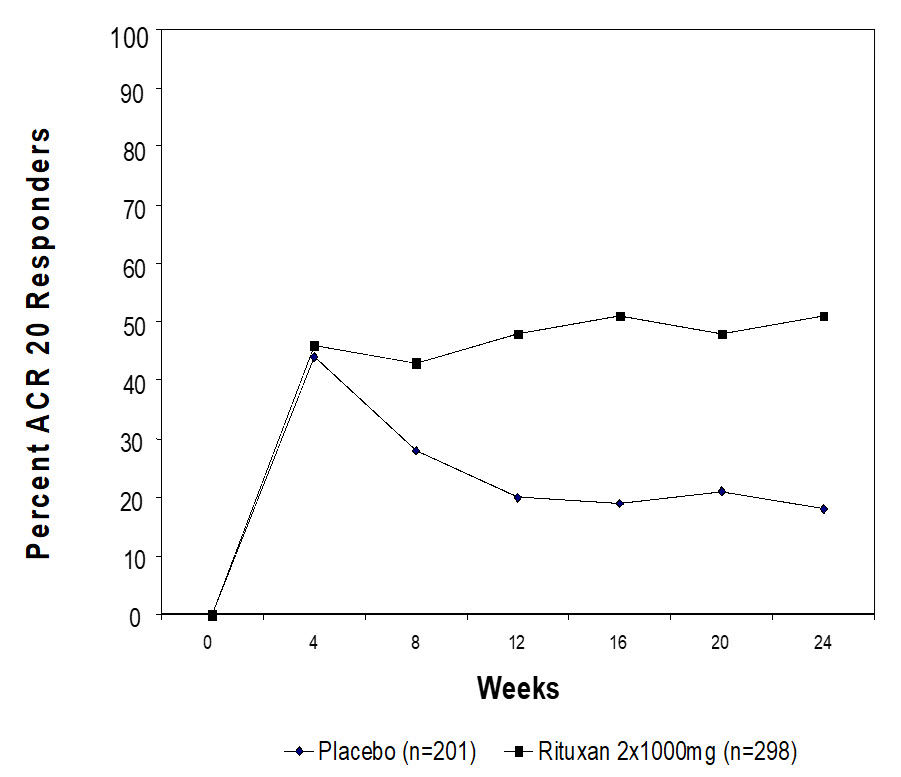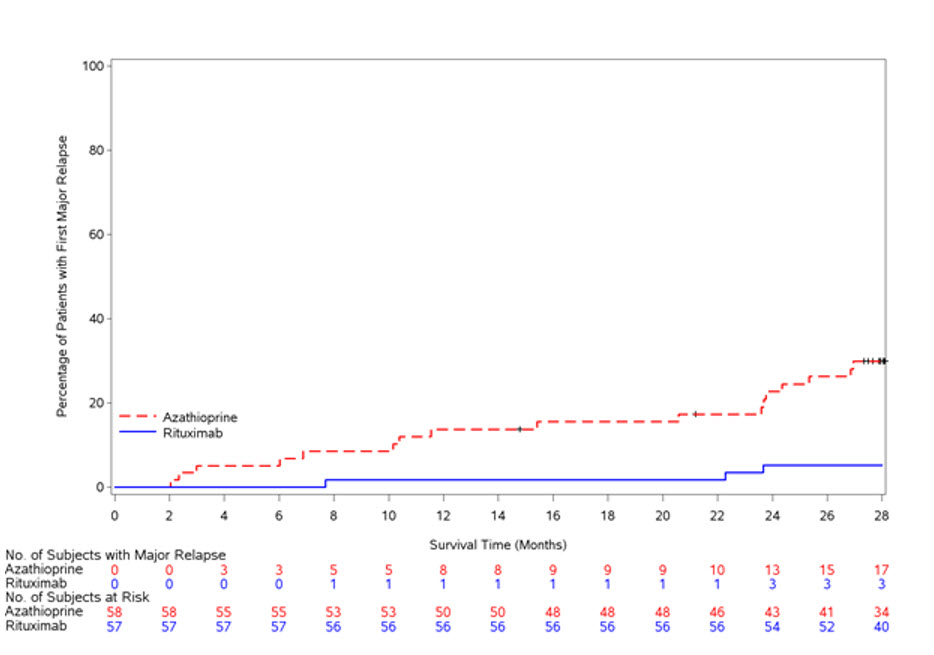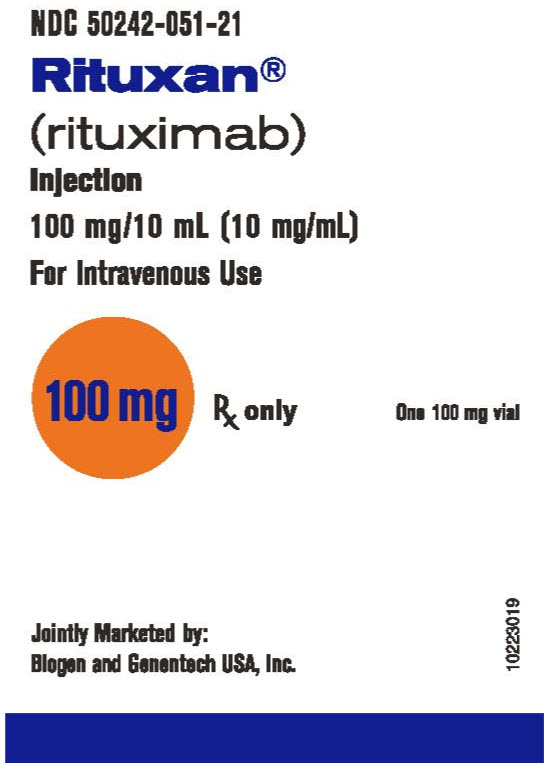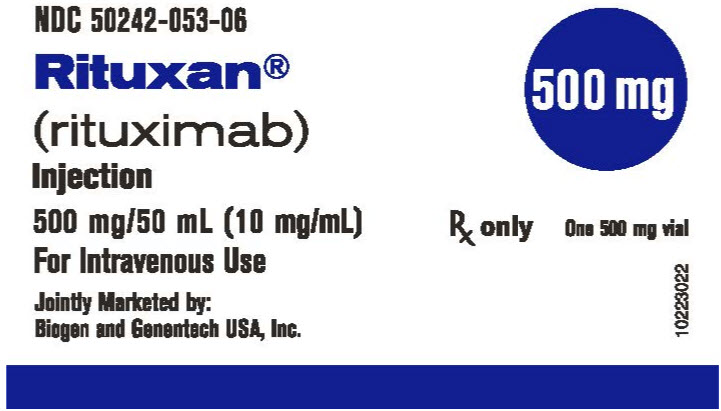 DRUG LABEL: Rituxan
NDC: 50242-051 | Form: INJECTION, SOLUTION
Manufacturer: Genentech, Inc.
Category: prescription | Type: HUMAN PRESCRIPTION DRUG LABEL
Date: 20250106

ACTIVE INGREDIENTS: RITUXIMAB 10 mg/1 mL
INACTIVE INGREDIENTS: SODIUM CHLORIDE 9 mg/1 mL; TRISODIUM CITRATE DIHYDRATE 7.35 mg/1 mL; POLYSORBATE 80 0.7 mg/1 mL; WATER

HIGHLIGHTS OF PRESCRIBING INFORMATION

These highlights do not include all the information needed to use RITUXAN safely and effectively. See full prescribing information for RITUXAN.
RITUXAN® (rituximab) injection, for intravenous use
Initial U.S. Approval: 1997

WARNING: FATAL INFUSION-RELATED REACTIONS, SEVERE MUCOCUTANEOUS REACTIONS, HEPATITIS B VIRUS REACTIVATION and PROGRESSIVE MULTIFOCAL LEUKOENCEPHALOPATHY

See full prescribing information for complete boxed warning.

- Fatal infusion-related reactions within 24 hours of RITUXAN infusion; approximately 80% of fatal reactions occurred with first infusion. Monitor patients and discontinue RITUXAN infusion for severe reactions (5.1).
- Severe mucocutaneous reactions, some with fatal outcomes (5.2).
- Hepatitis B virus (HBV) reactivation, in some cases resulting in fulminant hepatitis, hepatic failure, and death (5.3).
- Progressive multifocal leukoencephalopathy (PML) resulting in death (5.4).

RECENT MAJOR CHANGES

Indications and Usage (1.1) | 12/2021
Dosage and Administration, Important Dosing Information (2.1) | 12/2021
Dosage and Administration, NHL (2.2.) | 12/2021
Dosage and Administration, Premedication and Prophylactic Medication (2.8) | 12/2021
Dosage and Administration, Administration and Storage (2.9) | 6/2021
Warnings and Precautions, Infusion-Related Reactions (5.1) | 12/2021

1 INDICATIONS AND USAGE

RITUXAN is a CD20-directed cytolytic antibody indicated for the treatment of:

- Adult patients with Non-Hodgkin's Lymphoma (NHL) (1.1).
  - Relapsed or refractory, low grade or follicular, CD20-positive B-cell NHL as a single agent.
  - Previously untreated follicular, CD20-positive, B-cell NHL in combination with first line chemotherapy and, in patients achieving a complete or partial response to a rituximab product in combination with chemotherapy, as single-agent maintenance therapy.
  - Non-progressing (including stable disease), low-grade, CD20-positive, B-cell NHL as a single agent after first-line cyclophosphamide, vincristine, and prednisone (CVP) chemotherapy.
  - Previously untreated diffuse large B-cell, CD20-positive NHL in combination with (cyclophosphamide, doxorubicin, vincristine, and prednisone) (CHOP) or other anthracycline-based chemotherapy regimens.
- Pediatric patients aged 6 months and older with mature B-cell NHL and mature B-cell acute leukemia (B-AL) (1.1)
  - Previously untreated, advanced stage, CD20-positive, diffuse large B-cell lymphoma (DLBCL), Burkitt lymphoma (BL), Burkitt-like lymphoma (BLL) or mature B-cell acute leukemia (B-AL) in combination with chemotherapy.
- Adult patients with Chronic Lymphocytic Leukemia (CLL) (1.2).
  - Previously untreated and previously treated CD20-positive CLL in combination with fludarabine and cyclophosphamide (FC).
- Rheumatoid Arthritis (RA) in combination with methotrexate in adult patients with moderately-to severely-active RA who have inadequate response to one or more TNF antagonist therapies (1.3).
- Granulomatosis with Polyangiitis (GPA) (Wegener's Granulomatosis) and Microscopic Polyangiitis (MPA) in adult and pediatric patients 2 years of age and older in combination with glucocorticoids (1.4).
- Moderate to severe Pemphigus Vulgaris (PV) in adult patients (1.5).

2 DOSAGE AND ADMINISTRATION

- Administer only as an intravenous infusion (2.1).
- Do not administer as an intravenous push or bolus (2.1).
- RITUXAN should only be administered by a healthcare professional with appropriate medical support to manage severe infusion-related reactions that can be fatal if they occur. (2.1).
- The dose for adult and pediatric B-cell NHL is 375 mg/m^2 (2.2).
- The dose for CLL is 375 mg/m^2 in the first cycle and 500 mg/m^2 in cycles 2–6, in combination with FC, administered every 28 days (2.3).
- The dose as a component of Zevalin® (ibritumomab tiuxetan) Therapeutic Regimen is 250 mg/m^2 (2.4).
- The dose for RA in combination with methotrexate is two-1,000 mg intravenous infusions separated by 2 weeks (one course) every 24 weeks or based on clinical evaluation, but not sooner than every 16 weeks. Methylprednisolone 100 mg intravenous or equivalent glucocorticoid is recommended 30 minutes prior to each infusion (2.5).
- The induction dose for adult patients with active GPA and MPA in combination with glucocorticoids is 375 mg/m^2 once weekly for 4 weeks. The follow up dose for adult patients with GPA and MPA who have achieved disease control with induction treatment, in combination with glucocorticoids is two 500 mg intravenous infusions separated by two weeks, followed by a 500 mg intravenous infusion every 6 months thereafter based on clinical evaluation (2.6).
- The induction dose for pediatric patients with GPA and MPA in combination with glucocorticoids is 375 mg/m^2 once weekly for 4 weeks. The follow up dose for pediatric patients with GPA and MPA who have achieved disease control with induction treatment, in combination with glucocorticoids is two 250 mg/m^2 intravenous infusions separated by two weeks, followed by a 250 mg/m^2 intravenous infusion every 6 months thereafter based on clinical evaluation (2.6).
- The dose for PV is two-1,000 mg intravenous infusions separated by 2 weeks in combination with a tapering course of glucocorticoids, then a 500 mg intravenous infusion at Month 12 and every 6 months thereafter or based on clinical evaluation. Dose upon relapse is a 1,000 mg intravenous infusion with considerations to resume or increase the glucocorticoid dose based on clinical evaluation. Subsequent infusions may be no sooner than 16 weeks after the previous infusion (2.7). Methylprednisolone 100 mg intravenous or equivalent glucocorticoid is recommended 30 minutes prior to each infusion (2.8).

3 DOSAGE FORMS AND STRENGTHS

- Injection: 100 mg/10 mL (10 mg/mL) and 500 mg/50 mL (10 mg/mL) solution in single-dose vials (3)

4 CONTRAINDICATIONS

None (4)

5 WARNINGS AND PRECAUTIONS

- Tumor lysis syndrome: Administer aggressive intravenous hydration, anti-hyperuricemic agents, monitor renal function (5.5).
- Infections: Withhold RITUXAN and institute appropriate anti-infective therapy (5.6).
- Cardiac adverse reactions: Discontinue infusions in case of serious or life-threatening events (5.7).
- Renal toxicity: Discontinue in patients with rising serum creatinine or oliguria (5.8).
- Bowel obstruction and perforation: Consider and evaluate for abdominal pain, vomiting, or related symptoms (5.9).
- Immunizations: Live virus vaccinations prior to or during RITUXAN treatment not recommended (5.10).
- Embryo-Fetal toxicity: Can cause fetal harm. Advise females of reproductive potential of the potential risk to a fetus and use of effective contraception (5.11).

6 ADVERSE REACTIONS

Most common adverse reactions in clinical trials were:

- NHL (greater than or equal to 25%): infusion-related reactions, fever, lymphopenia, chills, infection, and asthenia (6.1).
- Pediatric B-NHL/B-AL with chemotherapy (Grade 3 or higher greater than 15%): febrile neutropenia, stomatitis, enteritis, sepsis, alanine aminotransferase increased and hypokalemia (6.1).
- CLL (greater than or equal to 25%): infusion-related reactions and neutropenia (6.1).
- RA (greater than or equal to 10%): upper respiratory tract infection, nasopharyngitis, urinary tract infection, and bronchitis (other important adverse reactions include infusion-related reactions, serious infections, and cardiovascular events) (6.1).
- GPA and MPA (greater than or equal to 15 %): infections, nausea, diarrhea, headache, muscle spasms, anemia, peripheral edema, infusion-related reactions (6.1).
- PV (greater than or equal to 15%): infusion-related reactions, depression, upper respiratory tract infection/ nasopharyngitis, headache (other important adverse reactions include infections) (6.1).

To report SUSPECTED ADVERSE REACTIONS, contact Genentech at 1-888-835-2555 or FDA at 1-800-FDA-1088 or www.fda.gov/medwatch.

7 DRUG INTERACTIONS

Renal toxicity when used in combination with cisplatin (5.8).

8 USE IN SPECIFIC POPULATIONS

- Lactation: Advise not to breastfeed (8.2).
- Geriatric Use: In CLL patients older than 70 years of age, exploratory analyses suggest no benefit with the addition of RITUXAN to FC (8.5).

FULL PRESCRIBING INFORMATION

WARNING: FATAL INFUSION-RELATED REACTIONS, SEVERE MUCOCUTANEOUS REACTIONS, HEPATITIS B VIRUS REACTIVATION and PROGRESSIVE MULTIFOCAL LEUKOENCEPHALOPATHY

Infusion-Related Reactions

RITUXAN administration can result in serious, including fatal, infusion-related reactions. Deaths within 24 hours of RITUXAN infusion have occurred. Approximately 80% of fatal infusion reactions occurred in association with the first infusion. Monitor patients closely. Discontinue RITUXAN infusion for severe reactions and provide medical treatment for Grade 3 or 4 infusion-related reactions [see Warnings and Precautions (5.1), Adverse Reactions (6.1)].

Severe Mucocutaneous Reactions

Severe, including fatal, mucocutaneous reactions can occur in patients receiving RITUXAN [see Warnings and Precautions (5.2)].

Hepatitis B Virus (HBV) Reactivation

HBV reactivation can occur in patients treated with RITUXAN, in some cases resulting in fulminant hepatitis, hepatic failure, and death. Screen all patients for HBV infection before treatment initiation, and monitor patients during and after treatment with RITUXAN. Discontinue RITUXAN and concomitant medications in the event of HBV reactivation [see Warnings and Precautions (5.3)].

Progressive Multifocal Leukoencephalopathy (PML), including fatal PML, can occur in patients receiving RITUXAN [see Warnings and Precautions (5.4) and Adverse Reactions (6.1)].

1 INDICATIONS AND USAGE

1.1 Non–Hodgkin's Lymphoma (NHL)

RITUXAN is indicated for the treatment of adult patients with:

- Relapsed or refractory, low-grade or follicular, CD20-positive, B-cell NHL as a single agent.
- Previously untreated follicular, CD20-positive, B-cell NHL in combination with first line chemotherapy and, in patients achieving a complete or partial response to a rituximab product in combination with chemotherapy, as single-agent maintenance therapy.
- Non-progressing (including stable disease), low-grade, CD20-positive, B-cell NHL as a single agent after first-line cyclophosphamide, vincristine, and prednisone (CVP) chemotherapy.
- Previously untreated diffuse large B-cell, CD20-positive NHL in combination with cyclophosphamide, doxorubicin, vincristine, prednisone (CHOP) or other anthracycline-based chemotherapy regimens.

RITUXAN is indicated for the treatment of pediatric patients aged 6 months and older with:

- Previously untreated, advanced stage, CD20-positive diffuse large B-cell lymphoma (DLBCL), Burkitt lymphoma (BL), Burkitt-like lymphoma (BLL) or mature B-cell acute leukemia (B-AL) in combination with chemotherapy.

1.2 Chronic Lymphocytic Leukemia (CLL)

RITUXAN, in combination with fludarabine and cyclophosphamide (FC), is indicated for the treatment of adult patients with previously untreated and previously treated CD20-positive CLL.

1.3 Rheumatoid Arthritis (RA)

RITUXAN, in combination with methotrexate, is indicated for the treatment of adult patients with moderately- to severely-active rheumatoid arthritis who have had an inadequate response to one or more TNF antagonist therapies.

1.4 Granulomatosis with Polyangiitis (GPA) (Wegener's Granulomatosis) and Microscopic Polyangiitis (MPA)

RITUXAN, in combination with glucocorticoids, is indicated for the treatment of adult and pediatric patients 2 years of age and older with Granulomatosis with Polyangiitis (GPA) (Wegener's Granulomatosis) and Microscopic Polyangiitis (MPA).

1.5 Pemphigus Vulgaris (PV)

RITUXAN is indicated for the treatment of adult patients with moderate to severe pemphigus vulgaris.

2 DOSAGE AND ADMINISTRATION

2.1 Important Dosing Information

Administer only as an Intravenous Infusion [see Dosage and Administration (2.8)]. Do not administer as an intravenous push or bolus.

RITUXAN should only be administered by a healthcare professional with appropriate medical support to manage severe infusion-related reactions that can be fatal if they occur [see Warnings and Precautions (5.1)].

Premedicate before each infusion [see Dosage and Administration (2.8)].

Prior to First Infusion: Screen all patients for HBV infection by measuring HBsAg and anti-HBc before initiating treatment with RITUXAN [see Warnings and Precautions (5.3)]. Obtain complete blood counts (CBC) including platelets prior to the first dose.

During RITUXAN Therapy: In patients with lymphoid malignancies, during treatment with RITUXAN monotherapy, obtain complete blood counts (CBC) with differential and platelet counts prior to each RITUXAN course. During treatment with RITUXAN and chemotherapy, obtain CBC with differential and platelet counts at weekly to monthly intervals and more frequently in patients who develop cytopenias [see Adverse Reactions (6.1)]. In patients with RA, GPA or MPA, obtain CBC with differential and platelet counts at two to four month intervals during RITUXAN therapy. Continue to monitor for cytopenias after final dose and until resolution.

- First Infusion:
  Standard Infusion: Initiate infusion at a rate of 50 mg/hr. In the absence of infusion toxicity, increase infusion rate by 50 mg/hr increments every 30 minutes, to a maximum of 400 mg/hr.
  For Pediatric Patients with mature B-cell NHL/B-AL:
  Initiate infusion at a rate of 0.5 mg/kg/hr (maximum 50 mg/hr). In the absence of infusion toxicity, increase infusion rate by 0.5 mg/kg/hr every 30 minutes, to a maximum of 400 mg/hr.
- Subsequent Infusions: Standard Infusion: Initiate infusion at a rate of 100 mg/hr. In the absence of infusion toxicity, increase rate by 100 mg/hr increments at 30-minute intervals, to a maximum of 400 mg/hr.
  For Previously Untreated Follicular NHL and DLBCL adult patients:
  If patients did not experience a Grade 3 or 4 infusion-related adverse event during Cycle 1, a 90-minute infusion can be administered in Cycle 2 with a glucocorticoid-containing chemotherapy regimen.
  Initiate at a rate of 20% of the total dose given in the first 30 minutes and the remaining 80% of the total dose given over the next 60 minutes. If the 90-minute infusion is tolerated in Cycle 2, the same rate can be used when administering the remainder of the treatment regimen (through Cycle 6 or 8).
  Patients who have clinically significant cardiovascular disease or who have a circulating lymphocyte count greater than or equal to 5,000/mm^3 before Cycle 2 should not be administered the 90-minute infusion [see Clinical Studies (14.4)].
  For Pediatric Patients with mature B-cell NHL/B-AL:
  Initiate infusion rate of 1 mg/kg/hr (maximum 50 mg/hr). In the absence of infusion toxicity, increase rate by 1 mg/kg/hr every 30 minutes, to a maximum of 400 mg/hr.
- Interrupt the infusion or slow the infusion rate for infusion-related reactions [see Boxed Warning, Warnings and Precautions (5.1)]. Continue the infusion at one-half the previous rate upon improvement of symptoms.

2.2 Recommended Dose for Non-Hodgkin's Lymphoma (NHL)

The recommended dose is 375 mg/m^2 as an intravenous infusion according to the following schedules:

- Relapsed or Refractory, Low-Grade or Follicular, CD20-Positive, B-Cell NHL
  Administer once weekly for 4 or 8 doses.
- Retreatment for Relapsed or Refractory, Low-Grade or Follicular, CD20-Positive, B-Cell NHL
  Administer once weekly for 4 doses.
- Previously Untreated, Follicular, CD20-Positive, B-Cell NHL
  Administer on Day 1 of each cycle of chemotherapy for up to 8 doses. In patients with complete or partial response, initiate RITUXAN maintenance eight weeks following completion of a rituximab product in combination with chemotherapy. Administer RITUXAN as a single-agent every 8 weeks for 12 doses.
- Non-progressing, Low-Grade, CD20-Positive, B-Cell NHL, after first-line CVP chemotherapy
  Following completion of 6–8 cycles of CVP chemotherapy, administer once weekly for 4 doses at 6-month intervals to a maximum of 16 doses.
- Diffuse Large B-Cell NHL
  Administer on Day 1 of each cycle of chemotherapy for up to 8 infusions.
- Pediatric patients aged 6 months and older with previously untreated mature B-cell NHL/B-AL
  RITUXAN is given in combination with systemic Lymphome Malin B (LMB) chemotherapy. In total, six infusions of RITUXAN are given, two doses during each of the induction courses, COPDAM1 and COPDAM2, and one dose during each of the two consolidation courses of CYM/CYVE (for details see Table 1).

Table 1: Posology of RITUXAN Administration for Pediatric Mature B-cell NHL/B-AL
Cycle | Day of treatment | Administration details
Prephase (COP) | No RITUXAN given | -
Induction courses 1 and 2 (COPDAM1 and COPDAM2) | Day -2 1st and 3rd RITUXAN infusions | During the 1st induction course, prednisone is given as part of the chemotherapy course, and should be administered prior to RITUXAN.
 | Day 1 2nd and 4th RITUXAN infusions | RITUXAN will be given 48 hours after the first infusion of RITUXAN.
Consolidation courses 1 and 2 (CYM/CYVE) | Day 1 5th and 6th RITUXAN infusions | -
COP = Cyclophosphamide, Oncovin (vincristine), Prednisone; COPDAM = Cyclophosphamide, Oncovin (vincristine), Prednisolone, Adriamycin (doxorubicin), Methotrexate; CYM = CYtarabine (Aracytine, Ara-C), Methotrexate; CYVE = CYtarabine (Aracytine, Ara-C), VEposide (VP16)

2.3 Recommended Dose for Chronic Lymphocytic Leukemia (CLL)

The recommended dose is 375 mg/m^2 the day prior to the initiation of FC chemotherapy, then 500 mg/m^2 on Day 1 of cycles 2–6 (every 28 days).

2.4 Recommended Dose as a Component of Zevalin® for treatment of NHL

- When used as part of the Zevalin therapeutic regimen, infuse 250 mg/m^2 in accordance with the Zevalin package insert. Refer to the Zevalin package insert for full prescribing information regarding the Zevalin therapeutic regimen.

2.5 Recommended Dose for Rheumatoid Arthritis (RA)

- Administer RITUXAN as two-1,000 mg intravenous infusions separated by 2 weeks.
- Glucocorticoids administered as methylprednisolone 100 mg intravenous or its equivalent 30 minutes prior to each infusion are recommended to reduce the incidence and severity of infusion-related reactions.
- Subsequent courses should be administered every 24 weeks or based on clinical evaluation, but not sooner than every 16 weeks.
- RITUXAN is given in combination with methotrexate.

2.6 Recommended Dose for Granulomatosis with Polyangiitis (GPA) (Wegener's Granulomatosis) and Microscopic Polyangiitis (MPA)

Induction Treatment of Adult Patients with Active GPA/MPA

- Administer RITUXAN as a 375 mg/m^2 intravenous infusion once weekly for 4 weeks for patients with active GPA or MPA.
- Glucocorticoids administered as methylprednisolone 1,000 mg intravenously per day for 1 to 3 days followed by oral prednisone as per clinical practice. This regimen should begin within 14 days prior to or with the initiation of RITUXAN and may continue during and after the 4 week induction course of RITUXAN treatment.

Follow up Treatment of Adult Patients with GPA/MPA who have achieved disease control with induction treatment

- Administer RITUXAN as two 500 mg intravenous infusions separated by two weeks, followed by a 500 mg intravenous infusion every 6 months thereafter based on clinical evaluation.
- If induction treatment of active disease was with a rituximab product, initiate follow up treatment with RITUXAN within 24 weeks after the last induction infusion with a rituximab product or based on clinical evaluation, but no sooner than 16 weeks after the last induction infusion with a rituximab product.
- If induction treatment of active disease was with other standard of care immunosuppressants, initiate RITUXAN follow up treatment within the 4 week period that follows achievement of disease control.

Induction treatment of Pediatric Patients with Active GPA/MPA

- Administer RITUXAN as a 375 mg/m^2 intravenous infusion once weekly for 4 weeks.
- Prior to the first RITUXAN infusion, administer intravenous methylprednisolone 30 mg/kg (not to exceed 1g/day) once daily for 3 days.
- Following intravenous methylprednisolone administration, oral steroids should be continued per clinical practice.

Follow up Treatment of Pediatric Patients with GPA/MPA who have achieved disease control with induction treatment

- Administer RITUXAN as two 250 mg/m^2 intravenous infusions separated by two weeks, followed by a 250 mg/m^2 intravenous infusion every 6 months thereafter based on clinical evaluation.
- If induction treatment of active disease was with a rituximab product, initiate follow up treatment with RITUXAN within 24 weeks after the last induction infusion with a rituximab product or based on clinical evaluation, but no sooner than 16 weeks after the last induction infusion with a rituximab product.
- If induction treatment of active disease was with other standard of care immunosuppressants, initiate RITUXAN follow up treatment within the 4 week period following achievement of disease control.

2.7 Recommended Dose for Pemphigus Vulgaris (PV)

- Administer RITUXAN as two-1,000 mg intravenous infusions separated by 2 weeks in combination with a tapering course of glucocorticoids.
- Maintenance treatment
  Administer RITUXAN as a 500 mg intravenous infusion at Month 12 and every 6 months thereafter or based on clinical evaluation.
- Treatment of relapse
  Administer RITUXAN as a 1,000 mg intravenous infusion on relapse, and consider resuming or increasing the glucocorticoid dose based on clinical evaluation.

Subsequent infusions of RITUXAN may be administered no sooner than 16 weeks following the previous infusion.

2.8 Recommended Dose for Premedication and Prophylactic Medications

Premedicate with acetaminophen and an antihistamine before each infusion of RITUXAN. For adult patients administered RITUXAN according to the 90-minute infusion rate, the glucocorticoid component of their chemotherapy regimen should be administered prior to infusion [see Clinical Studies (14.4)].

For pediatric patients with mature B-cell NHL/B-AL, premedication with acetaminophen and H1 antihistamine (diphenhydramine or equivalent) should be administered 30 to 60 minutes before the start of each RITUXAN intravenous infusion.

For RA, GPA and MPA, and PV patients, methylprednisolone 100 mg intravenously or its equivalent is recommended 30 minutes prior to each infusion.

Provide prophylaxis treatment for Pneumocystis jirovecii pneumonia (PCP) and herpes virus infections for patients with CLL during treatment and for up to 12 months following treatment as appropriate [see Warnings and Precautions (5.6)].

PCP prophylaxis is also recommended for patients with GPA and MPA during treatment and for at least 6 months following the last RITUXAN infusion.

PCP prophylaxis should be considered for patients with PV during and following RITUXAN treatment.

2.9 Administration and Storage

Use appropriate aseptic technique. Parenteral drug products should be inspected visually for particulate matter and discoloration prior to administration. RITUXAN should be a clear, colorless liquid. Do not use vial if particulates or discoloration is present.

Administration

Use a sterile needle and syringe to prepare RITUXAN. Withdraw the necessary amount of RITUXAN and dilute to a final concentration of 1 mg/mL to 4 mg/mL in an infusion bag containing either 0.9% Sodium Chloride, USP, or 5% Dextrose Injection, USP. Gently invert the bag to mix the solution. Do not mix or dilute with other drugs. Discard any unused portion left in the vial.

Storage

Diluted RITUXAN solutions for infusion may be stored refrigerated at 2°C to 8°C (36°F to 46°F) for 24 hours. Diluted RITUXAN solutions for infusion have been shown to be stable for an additional 24 hours at room temperature. However, since RITUXAN solutions do not contain a preservative, diluted solutions should be stored refrigerated (2°C to 8°C). No incompatibilities between RITUXAN and polyvinylchloride or polyethylene bags have been observed.

3 DOSAGE FORMS AND STRENGTHS

Injection: RITUXAN is a colorless, clear solution for intravenous infusion:

- 100 mg/10 mL (10 mg/mL) in a single-dose vial
- 500 mg/50 mL (10 mg/mL) in a single-dose vial

4 CONTRAINDICATIONS

None.

5 WARNINGS AND PRECAUTIONS

5.1 Infusion-Related Reactions

RITUXAN can cause severe, including fatal, infusion-related reactions. Severe reactions typically occurred during the first infusion with time to onset of 30–120 minutes. RITUXAN-induced infusion-related reactions and sequelae include urticaria, hypotension, angioedema, hypoxia, bronchospasm, pulmonary infiltrates, acute respiratory distress syndrome, myocardial infarction, ventricular fibrillation, cardiogenic shock, anaphylactoid events, or death.

Premedicate patients with an antihistamine and acetaminophen prior to dosing. For RA, GPA and MPA, and PV patients, methylprednisolone 100 mg intravenously or its equivalent is recommended 30 minutes prior to each infusion. For pediatric patients with mature B-cell NHL/B-AL, administer prednisone as part of chemotherapy regimen prior to RITUXAN during induction and as needed for subsequent cycles [see Dosage and Administration (2.2 and 2.8)]. Institute medical management (e.g., glucocorticoids, epinephrine, bronchodilators, or oxygen) for infusion-related reactions as needed. Depending on the severity of the infusion-related reaction and the required interventions, temporarily or permanently discontinue RITUXAN. Resume infusion at a minimum 50% reduction in rate after symptoms have resolved. Closely monitor the following patients: those with pre-existing cardiac or pulmonary conditions, those who experienced prior cardiopulmonary adverse reactions, and those with high numbers of circulating malignant cells (greater than or equal to 25,000/mm^3) [see Warnings and Precautions (5.7), Adverse Reactions (6.1)].

5.2 Severe Mucocutaneous Reactions

Mucocutaneous reactions, some with fatal outcome, can occur in patients treated with RITUXAN. These reactions include paraneoplastic pemphigus, Stevens-Johnson syndrome, lichenoid dermatitis, vesiculobullous dermatitis, and toxic epidermal necrolysis. The onset of these reactions has been variable and includes reports with onset on the first day of RITUXAN exposure. Discontinue RITUXAN in patients who experience a severe mucocutaneous reaction. The safety of re-administration of RITUXAN to patients with severe mucocutaneous reactions has not been determined.

5.3 Hepatitis B Virus (HBV) Reactivation

Hepatitis B virus (HBV) reactivation, in some cases resulting in fulminant hepatitis, hepatic failure and death, can occur in patients treated with drugs classified as CD20-directed cytolytic antibodies, including RITUXAN. Cases have been reported in patients who are hepatitis B surface antigen (HBsAg) positive and also in patients who are HBsAg negative but are hepatitis B core antibody (anti-HBc) positive. Reactivation also has occurred in patients who appear to have resolved hepatitis B infection (i.e., HBsAg negative, anti-HBc positive and hepatitis B surface antibody [anti-HBs] positive).

HBV reactivation is defined as an abrupt increase in HBV replication manifesting as a rapid increase in serum HBV DNA levels or detection of HBsAg in a person who was previously HBsAg negative and anti-HBc positive. Reactivation of HBV replication is often followed by hepatitis, i.e., increase in transaminase levels. In severe cases increase in bilirubin levels, liver failure, and death can occur.

Screen all patients for HBV infection by measuring HBsAg and anti-HBc before initiating treatment with RITUXAN. For patients who show evidence of prior hepatitis B infection (HBsAg positive [regardless of antibody status] or HBsAg negative but anti-HBc positive), consult with physicians with expertise in managing hepatitis B regarding monitoring and consideration for HBV antiviral therapy before and/or during RITUXAN treatment.

Monitor patients with evidence of current or prior HBV infection for clinical and laboratory signs of hepatitis or HBV reactivation during and for several months following RITUXAN therapy. HBV reactivation has been reported up to 24 months following completion of RITUXAN therapy.

In patients who develop reactivation of HBV while on RITUXAN, immediately discontinue RITUXAN and any concomitant chemotherapy, and institute appropriate treatment. Insufficient data exist regarding the safety of resuming RITUXAN treatment in patients who develop HBV reactivation. Resumption of RITUXAN treatment in patients whose HBV reactivation resolves should be discussed with physicians with expertise in managing HBV.

5.4 Progressive Multifocal Leukoencephalopathy (PML)

JC virus infection resulting in PML and death can occur in RITUXAN-treated patients with hematologic malignancies or with autoimmune diseases. The majority of patients with hematologic malignancies diagnosed with PML received RITUXAN in combination with chemotherapy or as part of a hematopoietic stem cell transplant. The patients with autoimmune diseases had prior or concurrent immunosuppressive therapy. Most cases of PML were diagnosed within 12 months of their last infusion of RITUXAN.

Consider the diagnosis of PML in any patient presenting with new-onset neurologic manifestations. Evaluation of PML includes, but is not limited to, consultation with a neurologist, brain MRI, and lumbar puncture.

Discontinue RITUXAN and consider discontinuation or reduction of any concomitant chemotherapy or immunosuppressive therapy in patients who develop PML.

5.5 Tumor Lysis Syndrome (TLS)

Acute renal failure, hyperkalemia, hypocalcemia, hyperuricemia, or hyperphosphatemia from tumor lysis, sometimes fatal, can occur within 12–24 hours after the first infusion of RITUXAN in patients with NHL. A high number of circulating malignant cells (greater than or equal to 25,000/mm^3) or high tumor burden, confers a greater risk of TLS.

Administer aggressive intravenous hydration and anti-hyperuricemic therapy in patients at high risk for TLS. Correct electrolyte abnormalities, monitor renal function and fluid balance, and administer supportive care, including dialysis as indicated. [see Warnings and Precautions (5.8)].

5.6 Infections

Serious, including fatal, bacterial, fungal, and new or reactivated viral infections can occur during and following the completion of RITUXAN-based therapy. Infections have been reported in some patients with prolonged hypogammaglobulinemia (defined as hypogammaglobulinemia greater than 11 months after rituximab exposure). New or reactivated viral infections included cytomegalovirus, herpes simplex virus, parvovirus B19, varicella zoster virus, West Nile virus, and hepatitis B and C. Discontinue RITUXAN for serious infections and institute appropriate anti-infective therapy [see Adverse Reactions (6.1, 6.3)]. RITUXAN is not recommended for use in patients with severe, active infections.

5.7 Cardiovascular Adverse Reactions

Cardiac adverse reactions, including ventricular fibrillation, myocardial infarction, and cardiogenic shock may occur in patients receiving RITUXAN. Discontinue infusions for serious or life-threatening cardiac arrhythmias. Perform cardiac monitoring during and after all infusions of RITUXAN for patients who develop clinically significant arrhythmias, or who have a history of arrhythmia or angina [see Adverse Reactions (6.1)].

5.8 Renal Toxicity

Severe, including fatal, renal toxicity can occur after RITUXAN administration in patients with NHL. Renal toxicity has occurred in patients who experience tumor lysis syndrome and in patients with NHL administered concomitant cisplatin therapy during clinical trials. The combination of cisplatin and RITUXAN is not an approved treatment regimen. Monitor closely for signs of renal failure and discontinue RITUXAN in patients with a rising serum creatinine or oliguria [see Warnings and Precautions (5.5)].

5.9 Bowel Obstruction and Perforation

Abdominal pain, bowel obstruction and perforation, in some cases leading to death, can occur in patients receiving RITUXAN in combination with chemotherapy. In postmarketing reports, the mean time to documented gastrointestinal perforation was 6 (range 1–77) days in patients with NHL. Evaluate if symptoms of obstruction such as abdominal pain or repeated vomiting occur.

5.10 Immunization

The safety of immunization with live viral vaccines following RITUXAN therapy has not been studied and vaccination with live virus vaccines is not recommended before or during treatment.

For patients treated with RITUXAN, physicians should review the patient's vaccination status and patients should, if possible, be brought up-to-date with all immunizations in agreement with current immunization guidelines prior to initiating RITUXAN and administer non live vaccines at least 4 weeks prior to a course of RITUXAN.

The effect of RITUXAN on immune responses was assessed in a randomized, controlled study in patients with RA treated with RITUXAN and methotrexate (MTX) compared to patients treated with MTX alone.

A response to pneumococcal vaccination (a T-cell independent antigen) as measured by an increase in antibody titers to at least 6 of 12 serotypes was lower in patients treated with RITUXAN plus MTX as compared to patients treated with MTX alone (19% vs. 61%). A lower proportion of patients in the RITUXAN plus MTX group developed detectable levels of anti-keyhole limpet hemocyanin antibodies (a novel protein antigen) after vaccination compared to patients on MTX alone (47% vs. 93%).

A positive response to tetanus toxoid vaccine (a T-cell dependent antigen with existing immunity) was similar in patients treated with RITUXAN plus MTX compared to patients on MTX alone (39% vs. 42%). The proportion of patients maintaining a positive Candida skin test (to evaluate delayed type hypersensitivity) was also similar (77% of patients on RITUXAN plus MTX vs. 70% of patients on MTX alone).

Most patients in the RITUXAN-treated group had B-cell counts below the lower limit of normal at the time of immunization. The clinical implications of these findings are not known.

5.11 Embryo-Fetal Toxicity

Based on human data, RITUXAN can cause fetal harm due to B-cell lymphocytopenia in infants exposed to rituximab in-utero. Advise pregnant women of the potential risk to a fetus. Advise females of reproductive potential to use effective contraception while receiving RITUXAN and for 12 months after the last dose [see Use in Specific Populations (8.1, 8.3)].

5.12 Concomitant Use with Other Biologic Agents and DMARDS other than Methotrexate in RA, GPA and MPA, PV

Limited data are available on the safety of the use of biologic agents or disease modifying antirheumatic drugs (DMARDs) other than methotrexate in RA patients exhibiting peripheral B-cell depletion following treatment with rituximab. Observe patients closely for signs of infection if biologic agents and/or DMARDs are used concomitantly. Use of concomitant immunosuppressants other than corticosteroids has not been studied in GPA or MPA or PV patients exhibiting peripheral B-cell depletion following treatment with RITUXAN.

5.13 Use in RA Patients Who Have Not Had Prior Inadequate Response to Tumor Necrosis Factor (TNF) Antagonists

While the efficacy of RITUXAN was supported in four controlled trials in patients with RA with prior inadequate responses to non-biologic DMARDs, and in a controlled trial in MTX-naïve patients, a favorable risk-benefit relationship has not been established in these populations. The use of RITUXAN in patients with RA who have not had prior inadequate response to one or more TNF antagonists is not recommended [see Clinical Studies (14.6)].

6 ADVERSE REACTIONS

The following clinically significant adverse reactions are discussed in greater detail in other sections of the labeling:

- Infusion-related reactions [see Warnings and Precautions (5.1)]
- Severe mucocutaneous reactions [see Warnings and Precautions (5.2)]
- Hepatitis B reactivation with fulminant hepatitis [see Warnings and Precautions (5.3)]
- Progressive multifocal leukoencephalopathy [see Warnings and Precautions (5.4)]
- Tumor lysis syndrome [see Warnings and Precautions (5.5)]
- Infections [see Warnings and Precautions (5.6)]
- Cardiovascular adverse reactions [see Warnings and Precautions (5.7)]
- Renal toxicity [see Warnings and Precautions (5.8)]
- Bowel obstruction and perforation [see Warnings and Precautions (5.9)]

6.1 Clinical Trials Experience

Because clinical trials are conducted under widely varying conditions, adverse reaction rates observed in the clinical trials of a drug cannot be directly compared to rates in the clinical trials of another drug and may not reflect the rates observed in clinical practice.

B-Cell Malignancies

The data described below reflect exposure to RITUXAN in 3092 patients, with exposures ranging from a single infusion up to 2 years. RITUXAN was studied in both single-arm and controlled trials (n=356 and n=2427). The population included 1180 patients with low grade or follicular lymphoma, 927 patients with DLBCL, 676 patients with CLL, and 309 pediatric patients with mature B-cell NHL/B-AL. Most NHL patients received RITUXAN as an infusion of 375 mg/m^2 per infusion, given as a single agent weekly for up to 8 doses, in combination with chemotherapy for up to 8 doses, or following chemotherapy for up to 16 doses. Pediatric patients received 6 total doses of RITUXAN or a non-U.S. licensed rituximab in combination with chemotherapy. CLL patients received RITUXAN 375 mg/m^2 as an initial infusion followed by 500 mg/m^2 for up to 5 doses, in combination with fludarabine and cyclophosphamide. Seventy-one percent of CLL patients received 6 cycles and 90% received at least 3 cycles of RITUXAN-based therapy.

The most common adverse reactions of RITUXAN (incidence greater than or equal to 25%) observed in clinical trials of patients with NHL were infusion-related reactions, fever, lymphopenia, chills, infection, and asthenia.

The most common adverse reactions of RITUXAN (incidence greater than or equal to 25%) observed in clinical trials of patients with CLL were: infusion-related reactions and neutropenia.

Infusion-Related Reactions

In the majority of patients with NHL, infusion-related reactions consisting of fever, chills/rigors, nausea, pruritus, angioedema, hypotension, headache, bronchospasm, urticaria, rash, vomiting, myalgia, dizziness, or hypertension occurred during the first RITUXAN infusion. Infusion-related reactions typically occurred within 30 to 120 minutes of beginning the first infusion and resolved with slowing or interruption of the RITUXAN infusion and with supportive care (diphenhydramine, acetaminophen, and intravenous saline). The incidence of infusion-related reactions was highest during the first infusion (77%) and decreased with each subsequent infusion. [see Warnings and Precautions (5.1)]. In adult patients with previously untreated follicular NHL or previously untreated DLBCL, who did not experience a Grade 3 or 4 infusion-related reaction in Cycle 1 and received a 90-minute infusion of RITUXAN at Cycle 2, the incidence of Grade 3-4 infusion reactions on the day of, or day after the infusion was 1.1% (95% CI [0.3%, 2.8%]). For Cycles 2-8, the incidence of Grade 3-4 infusion-related reactions on the day of or day after the 90-minute infusion, was 2.8% (95% CI [1.3%, 5.0%]). In pediatric patients, the incidence of grade 3 infusion reactions was 3.4% with the first infusion and 1% for subsequent infusions. One patient experienced a grade 4 infusion reaction with the fifth infusion. [see Warnings and Precautions (5.1), Clinical Studies (14.4)].

Infections

Serious infections (NCI CTCAE Grade 3 or 4), including sepsis, occurred in less than 5% of patients with NHL in the single-arm studies. The overall incidence of infections was 31% (bacterial 19%, viral 10%, unknown 6%, and fungal 1%). [see Warnings and Precautions (5.6)].

In randomized, controlled studies where RITUXAN was administered following chemotherapy for the treatment of follicular or low-grade NHL, the rate of infection was higher among patients who received RITUXAN. In diffuse large B-cell lymphoma patients, viral infections occurred more frequently in those who received RITUXAN. In pediatric patients with mature B-cell NHL/B-AL, the rate of serious infections was higher, with an incidence of 32%, in those receiving RITUXAN or a non-U.S. licensed rituximab with chemotherapy.

Cytopenias and hypogammaglobulinemia

In patients with NHL receiving rituximab monotherapy, NCI-CTC Grade 3 and 4 cytopenias were reported in 48% of patients. These included lymphopenia (40%), neutropenia (6%), leukopenia (4%), anemia (3%), and thrombocytopenia (2%). The median duration of lymphopenia was 14 days (range, 1–588 days) and of neutropenia was 13 days (range, 2–116 days). A single occurrence of transient aplastic anemia (pure red cell aplasia) and two occurrences of hemolytic anemia following RITUXAN therapy occurred during the single-arm studies.

In studies of monotherapy, RITUXAN-induced B-cell depletion occurred in 70% to 80% of patients with NHL. Decreased IgM and IgG serum levels occurred in 14% of these patients.

In CLL trials, the frequency of prolonged neutropenia and late-onset neutropenia was higher in patients treated with R-FC compared to patients treated with FC. Prolonged neutropenia is defined as Grade 3-4 neutropenia that has not resolved between 24 and 42 days after the last dose of study treatment. Late-onset neutropenia is defined as Grade 3-4 neutropenia starting at least 42 days after the last treatment dose.

In patients with previously untreated CLL, the frequency of prolonged neutropenia was 8.5% for patients who received R-FC (n=402) and 5.8% for patients who received FC (n=398). In patients who did not have prolonged neutropenia, the frequency of late-onset neutropenia was 14.8% of 209 patients who received R-FC and 4.3% of 230 patients who received FC.

For patients with previously treated CLL, the frequency of prolonged neutropenia was 24.8% for patients who received R-FC (n=274) and 19.1% for patients who received FC (n=274). In patients who did not have prolonged neutropenia, the frequency of late-onset neutropenia was 38.7% in 160 patients who received R-FC and 13.6% of 147 patients who received FC.

Relapsed or Refractory, Low-Grade NHL

Adverse reactions presented in Table 2 occurred in 356 patients with relapsed or refractory, low-grade or follicular, CD20-positive, B-cell NHL treated in single-arm studies of RITUXAN administered as a single agent [see Clinical Studies (14.1)]. Most patients received RITUXAN 375 mg/m^2 weekly for 4 doses.

Table 2 Incidence of Adverse Reactions in greater than or equal to 5% of Patients with Relapsed or Refractory, Low-Grade or Follicular NHL, Receiving Single-agent RITUXAN (N=356) [Adverse reactions observed up to 12 months following RITUXAN.] , [Adverse reactions graded for severity by NCI-CTC criteria.]
 | All Grades (%) | Grade 3 and 4 (%)
Any Adverse Reactions | 99 | 57
Body as a Whole | 86 | 10
Fever | 53 | 1
Chills | 33 | 3
Infection | 31 | 4
Asthenia | 26 | 1
Headache | 19 | 1
Abdominal Pain | 14 | 1
Pain | 12 | 1
Back Pain | 10 | 1
Throat Irritation | 9 | 0
Flushing | 5 | 0
Heme and Lymphatic System | 67 | 48
Lymphopenia | 48 | 40
Leukopenia | 14 | 4
Neutropenia | 14 | 6
Thrombocytopenia | 12 | 2
Anemia | 8 | 3
Skin and Appendages | 44 | 2
Night Sweats | 15 | 1
Rash | 15 | 1
Pruritus | 14 | 1
Urticaria | 8 | 1
Respiratory System | 38 | 4
Increased Cough | 13 | 1
Rhinitis | 12 | 1
Bronchospasm | 8 | 1
Dyspnea | 7 | 1
Sinusitis | 6 | 0
Metabolic and Nutritional Disorders | 38 | 3
Angioedema | 11 | 1
Hyperglycemia | 9 | 1
Peripheral Edema | 8 | 0
LDH Increase | 7 | 0
Digestive System | 37 | 2
Nausea | 23 | 1
Diarrhea | 10 | 1
Vomiting | 10 | 1
Nervous System | 32 | 1
Dizziness | 10 | 1
Anxiety | 5 | 1
Musculoskeletal System | 26 | 3
Myalgia | 10 | 1
Arthralgia | 10 | 1
Cardiovascular System | 25 | 3
Hypotension | 10 | 1
Hypertension | 6 | 1

In these single-arm RITUXAN studies, bronchiolitis obliterans occurred during and up to 6 months after RITUXAN infusion.

Previously Untreated, Low-Grade or Follicular, NHL

In NHL Study 4, patients in the R-CVP arm experienced a higher incidence of infusional toxicity and neutropenia compared to patients in the CVP arm. The following adverse reactions occurred more frequently (greater than or equal to 5%) in patients receiving R-CVP compared to CVP alone: rash (17% vs. 5%), cough (15% vs. 6%), flushing (14% vs. 3%), rigors (10% vs. 2%), pruritus (10% vs. 1%), neutropenia (8% vs. 3%), and chest tightness (7% vs. 1%). [see Clinical Studies (14.2)].

In NHL Study 5, detailed safety data collection was limited to serious adverse reactions, Grade greater than or equal to 2 infections, and Grade greater than or equal to 3 adverse reactions. In patients receiving RITUXAN as single-agent maintenance therapy following RITUXAN plus chemotherapy, infections were reported more frequently compared to the observation arm (37% vs. 22%). Grade 3-4 adverse reactions occurring at a higher incidence (greater than or equal to 2%) in the RITUXAN group were infections (4% vs. 1%) and neutropenia (4% vs. less than 1%).

In NHL Study 6, the following adverse reactions were reported more frequently (greater than or equal to 5%) in patients receiving RITUXAN following CVP compared to patients who received no further therapy: fatigue (39% vs. 14%), anemia (35% vs. 20%), peripheral sensory neuropathy (30% vs. 18%), infections (19% vs. 9%), pulmonary toxicity (18% vs. 10%), hepato-biliary toxicity (17% vs. 7%), rash and/or pruritus (17% vs. 5%), arthralgia (12% vs. 3%), and weight gain (11% vs. 4%). Neutropenia was the only Grade 3 or 4 adverse reaction that occurred more frequently (greater than or equal to 2%) in the RITUXAN arm compared with those who received no further therapy (4% vs. 1%). [see Clinical Studies (14.3)].

DLBCL

In NHL Studies 7 (NCT00003150) and 8, [see Clinical Studies (14.3)], the following adverse reactions, regardless of severity, were reported more frequently (greater than or equal to 5%) in patients age greater than or equal to 60 years receiving R-CHOP as compared to CHOP alone: pyrexia (56% vs. 46%), lung disorder (31% vs. 24%), cardiac disorder (29% vs. 21%), and chills (13% vs. 4%). Detailed safety data collection in these studies was primarily limited to Grade 3 and 4 adverse reactions and serious adverse reactions.

In NHL Study 8, a review of cardiac toxicity determined that supraventricular arrhythmias or tachycardia accounted for most of the difference in cardiac disorders (4.5% for R-CHOP vs. 1.0% for CHOP).

The following Grade 3 or 4 adverse reactions occurred more frequently among patients in the R-CHOP arm compared with those in the CHOP arm: thrombocytopenia (9% vs. 7%) and lung disorder (6% vs. 3%). Other Grade 3 or 4 adverse reactions occurring more frequently among patients receiving R-CHOP were viral infection (NHL Study 8), neutropenia (NHL Studies 8 and 9 (NCT00064116)), and anemia (NHL Study 9).

Pediatric Patients with DLBCL/BL/BLL/B-AL

The safety of RITUXAN administered in combination with LMB chemotherapy in pediatric patients was evaluated in NHL Study 11 [see Clinical Studies (14.2)], which included 309 patients treated with RITUXAN or non-U.S. licensed rituximab with chemotherapy and 164 patients treated with chemotherapy alone. Pediatric patients randomized to the LMB chemotherapy arm with RITUXAN or non-U.S.-licensed rituximab, or enrolled in the single arm part of the study, were administered RITUXAN or non-U.S. licensed rituximab intravenous at a dose of 375 mg/m^2 BSA and received a total of six infusions of RITUXAN (two during each of the two induction courses and one during each of the two consolidation courses of the LMB scheme).

In NHL Study 11, serious adverse reactions occurred in 55% of patients who received RITUXAN or non-US licensed rituximab with LMB chemotherapy. Serious adverse reactions in more than or equal to 5% included febrile neutropenia (15%), stomatitis (11%), sepsis (8%), and device-related infections (5%). Fatal adverse reactions occurred in 3% of patients, most often due to sepsis (2%), and included one case of second primary malignancy. Permanent discontinuation of RITUXAN or non- U.S. licensed rituximab occurred in 2% of patients. Adverse reactions which resulted in permanent discontinuation of RITUXAN or non-U.S. licensed rituximab included infection, anaphylaxis, hypotension, and leukoencephalopathy. Detailed safety data collection in this study was primarily limited to Grade 3 and 4 adverse reactions and serious adverse reactions.

Table 3 shows Grade 3 and higher adverse reactions (greater than or equal to 10%) in the RITUXAN or non-U.S.-licensed rituximab with chemotherapy or chemotherapy alone arms in patients with untreated mature B-cell NHL/B-AL.

The most common (greater than or equal to 15%) Grade 3 and higher adverse reactions were febrile neutropenia, stomatitis, enteritis, sepsis, alanine aminotransferase increased, and hypokalemia.

Table 3 Grade 3 or Higher Adverse Reactions Occurring (greater than or equal to 10%) in Pediatric Patients treated with RITUXAN with Chemotherapy or Chemotherapy Alone
Adverse Reaction | RITUXAN + Chemotherapy N=162 (%) | Chemotherapy N=153 (%)
Blood and lymphatic system disorders
Febrile Neutropenia | 93 | 91
Gastrointestinal disorders
Stomatitis | 80 | 75
Enteritis | 24 | 16
Investigations
Alanine aminotransferase increased | 19 | 14
Aspartate aminotransferase increased | 11 | 7
Infections and infestations
Sepsis | 18 [Includes fatal adverse reaction] | 13
Device Related infection | 13 | 12
Lung Infection | 12 | 9
Enterocolitis infections | 9 | 12
Metabolism and nutrition disorders
Hypokalemia | 16 | 13
Decreased appetite | 11 | 5

CLL

The data below reflect exposure to RITUXAN in combination with fludarabine and cyclophosphamide in 676 patients with CLL in CLL Study 1 (NCT00281918) or CLL Study 2 (NCT00090051) [see Clinical Studies (14.5)]. The age range was 30–83 years and 71% were men. Detailed safety data collection in CLL Study 1 was limited to Grade 3 and 4 adverse reactions and serious adverse reactions.

Infusion-related adverse reactions were defined by any of the following adverse events occurring during or within 24 hours of the start of infusion: nausea, pyrexia, chills, hypotension, vomiting, and dyspnea.

In CLL Study 1, the following Grade 3 and 4 adverse reactions occurred more frequently in R-FC-treated patients compared to FC-treated patients: infusion-related reactions (9% in R-FC arm), neutropenia (30% vs. 19%), febrile neutropenia (9% vs. 6%), leukopenia (23% vs. 12%), and pancytopenia (3% vs. 1%).

In CLL Study 2, the following Grade 3 or 4 adverse reactions occurred more frequently in R-FC-treated patients compared to FC-treated patients: infusion-related reactions (7% in R-FC arm), neutropenia (49% vs. 44%), febrile neutropenia (15% vs. 12%), thrombocytopenia (11% vs. 9%), hypotension (2% vs. 0%), and hepatitis B (2% vs. < 1%). Fifty-nine percent of R-FC-treated patients experienced an infusion-related reaction of any severity.

Rheumatoid Arthritis

The data presented below reflect the experience in 2578 RA patients treated with RITUXAN in controlled and long-term studies [Pooled studies: NCT00074438, NCT00422383, NCT00468546, NCT00299130, NCT00282308, NCT00266227, NCT02693210, NCT02093026 and NCT02097745.] with a total exposure of 5014 patient-years.

Among all exposed patients, adverse reactions reported in greater than 10% of patients include infusion-related reactions, upper respiratory tract infection, nasopharyngitis, urinary tract infection, and bronchitis.

In placebo-controlled studies, patients received 2 × 500 mg or 2 × 1,000 mg intravenous infusions of RITUXAN or placebo, in combination with methotrexate, during a 24-week period. From these studies, 938 patients treated with RITUXAN (2 × 1,000 mg) or placebo have been pooled (see Table 4). Adverse reactions reported in greater than or equal to 5% of patients were hypertension, nausea, upper respiratory tract infection, arthralgia, pyrexia and pruritus (see Table 4). The rates and types of adverse reactions in patients who received RITUXAN 2 × 500 mg were similar to those observed in patients who received RITUXAN 2 × 1,000 mg.

Table 4 [These data are based on 938 patients treated in Phase 2 and 3 studies of RITUXAN (2 × 1,000 mg) or placebo administered in combination with methotrexate.] Incidence of All Adverse Reactions [Coded using MedDRA.] Occurring in greater than or equal to 2% and at Least 1% Greater than Placebo Among Rheumatoid Arthritis Patients in Clinical Studies Up to Week 24 (Pooled)
Adverse Reactions | Placebo + MTX N=398 n (%) | RITUXAN + MTX N=540 n (%)
Hypertension | 21 (5) | 43 (8)
Nausea | 19 (5) | 41 (8)
Upper Respiratory Tract Infection | 23 (6) | 37 (7)
Arthralgia | 14 (4) | 31 (6)
Pyrexia | 8 (2) | 27 (5)
Pruritus | 5 (1) | 26 (5)
Chills | 9 (2) | 16 (3)
Dyspepsia | 3 (< 1) | 16 (3)
Rhinitis | 6 (2) | 14 (3)
Paresthesia | 3 (< 1) | 12 (2)
Urticaria | 3 (< 1) | 12 (2)
Abdominal Pain Upper | 4 (1) | 11 (2)
Throat Irritation | 0 (0) | 11 (2)
Anxiety | 5 (1) | 9 (2)
Migraine | 2 (< 1) | 9 (2)
Asthenia | 1 (< 1) | 9 (2)

Infusion-Related Reactions

In the RITUXAN RA pooled placebo-controlled studies, 32% of RITUXAN-treated patients experienced an adverse reaction during or within 24 hours following their first infusion, compared to 23% of placebo-treated patients receiving their first infusion. The incidence of adverse reactions during the 24-hour period following the second infusion, RITUXAN or placebo, decreased to 11% and 13%, respectively. Acute infusion-related reactions (manifested by fever, chills, rigors, pruritus, urticaria/rash, angioedema, sneezing, throat irritation, cough, and/or bronchospasm, with or without associated hypotension or hypertension) were experienced by 27% of RITUXAN-treated patients following their first infusion, compared to 19% of placebo-treated patients receiving their first placebo infusion. The incidence of these acute infusion-related reactions following the second infusion of RITUXAN or placebo decreased to 9% and 11%, respectively. Serious acute infusion-related reactions were experienced by less than 1% of patients in either treatment group. Acute infusion-related reactions required dose modification (stopping, slowing, or interruption of the infusion) in 10% and 2% of patients receiving rituximab or placebo, respectively, after the first course. The proportion of patients experiencing acute infusion-related reactions decreased with subsequent courses of RITUXAN. The administration of intravenous glucocorticoids prior to RITUXAN infusions reduced the incidence and severity of such reactions, however, there was no clear benefit from the administration of oral glucocorticoids for the prevention of acute infusion-related reactions. Patients in clinical studies also received antihistamines and acetaminophen prior to RITUXAN infusions.

Infections

In the pooled, placebo-controlled studies, 39% of patients in the RITUXAN group experienced an infection of any type compared to 34% of patients in the placebo group. The most common infections were nasopharyngitis, upper respiratory tract infections, urinary tract infections, bronchitis, and sinusitis.

The incidence of serious infections was 2% in the RITUXAN-treated patients and 1% in the placebo group.

In the experience with RITUXAN in 2578 RA patients, the rate of serious infections was 4.31 per 100 patient years. The most common serious infections (greater than or equal to 0.5%) were pneumonia or lower respiratory tract infections, cellulitis and urinary tract infections. Fatal serious infections included pneumonia, sepsis and colitis. Rates of serious infection remained stable in patients receiving subsequent courses. In 185 RITUXAN-treated RA patients with active disease, subsequent treatment with a biologic DMARD, the majority of which were TNF antagonists, did not appear to increase the rate of serious infection. Thirteen serious infections were observed in 186.1 patient years (6.99 per 100 patient years) prior to exposure and 10 were observed in 182.3 patient years (5.49 per 100 patient years) after exposure.

Cardiovascular Adverse Reactions

In the pooled, placebo-controlled studies, the proportion of patients with serious cardiovascular reactions was 1.7% and 1.3% in the RITUXAN and placebo treatment groups, respectively. Three cardiovascular deaths occurred during the double-blind period of the RA studies including all rituximab regimens (3/769 = 0.4%) as compared to none in the placebo treatment group (0/389).

In the experience with RITUXAN in 2578 RA patients, the rate of serious cardiac reactions was 1.93 per 100 patient years. The rate of myocardial infarction (MI) was 0.56 per 100 patient years (28 events in 26 patients), which is consistent with MI rates in the general RA population. These rates did not increase over three courses of RITUXAN.

Since patients with RA are at increased risk for cardiovascular events compared with the general population, patients with RA should be monitored throughout the infusion and RITUXAN should be discontinued in the event of a serious or life-threatening cardiac event.

Hypophosphatemia and hyperuricemia

In the pooled, placebo-controlled studies, newly-occurring hypophosphatemia (less than 2.0 mg/dl) was observed in 12% (67/540) of patients on RITUXAN versus 10% (39/398) of patients on placebo. Hypophosphatemia was more common in patients who received corticosteroids. Newly-occurring hyperuricemia (greater than 10 mg/dl) was observed in 1.5% (8/540) of patients on RITUXAN versus 0.3% (1/398) of patients on placebo.

In the experience with RITUXAN in RA patients, newly-occurring hypophosphatemia was observed in 21% (528/2570) of patients and newly-occurring hyperuricemia was observed in 2% (56/2570) of patients. The majority of the observed hypophosphatemia occurred at the time of the infusions and was transient.

Retreatment in Patients with RA

In the experience with RITUXAN in RA patients, 2578 patients have been exposed to RITUXAN and have received up to 10 courses of RITUXAN in RA clinical trials, with 1890, 1043, and 425 patients having received at least two, three, and four courses, respectively. Most of the patients who received additional courses did so 24 weeks or more after the previous course and none were retreated sooner than 16 weeks. The rates and types of adverse reactions reported for subsequent courses of RITUXAN were similar to rates and types seen for a single course of RITUXAN.

In RA Study 2, where all patients initially received RITUXAN, the safety profile of patients who were retreated with RITUXAN was similar to those who were retreated with placebo [see Clinical Studies (14.6), and Dosage and Administration (2.5)].

Granulomatosis with Polyangiitis (GPA) (Wegener's Granulomatosis) and Microscopic Polyangiitis (MPA)

Induction Treatment of Adult Patients with Active GPA/MPA (GPA/MPA Study 1)

The data presented below from GPA/MPA Study 1 (NCT00104299) reflect the experience in 197 adult patients with active GPA and MPA treated with RITUXAN or cyclophosphamide in a single controlled study, which was conducted in two phases: a 6 month randomized, double-blind, double-dummy, active-controlled remission induction phase and an additional 12 month remission maintenance phase [see Clinical Studies (14.7)]. In the 6-month remission induction phase, 197 patients with GPA and MPA were randomized to either RITUXAN 375 mg/ m^2 once weekly for 4 weeks plus glucocorticoids, or oral cyclophosphamide 2 mg/kg daily (adjusted for renal function, white blood cell count, and other factors) plus glucocorticoids to induce remission. Once remission was achieved or at the end of the 6 month remission induction period, the cyclophosphamide group received azathioprine to maintain remission. The RITUXAN group did not receive additional therapy to maintain remission. The primary analysis was at the end of the 6 month remission induction period and the safety results for this period are described below.

Adverse reactions presented below in Table 5 were adverse events which occurred at a rate of greater than or equal to 10% in the RITUXAN group. This table reflects experience in 99 GPA and MPA patients treated with RITUXAN, with a total of 47.6 patient-years of observation and 98 GPA and MPA patients treated with cyclophosphamide, with a total of 47.0 patient-years of observation. Infection was the most common category of adverse events reported (47-62%) and is discussed below.

Table 5 Incidence of All Adverse Reactions Occurring in greater than or equal to 10% of RITUXAN-treated Patients with active GPA and MPA in the GPA/MPA Study 1 Up to Month 6 [The study design allowed for crossover or treatment by best medical judgment, and 13 patients in each treatment group received a second therapy during the 6 month study period.]
Adverse Reaction | RITUXAN N=99 n (%) | Cyclophosphamide N=98 n (%)
Nausea | 18 (18%) | 20 (20%)
Diarrhea | 17 (17%) | 12 (12%)
Headache | 17 (17%) | 19 (19%)
Muscle spasms | 17 (17%) | 15 (15%)
Anemia | 16 (16%) | 20 (20%)
Peripheral edema | 16 (16%) | 6 (6%)
Insomnia | 14 (14%) | 12 (12%)
Arthralgia | 13 (13%) | 9 (9%)
Cough | 13 (13%) | 11 (11%)
Fatigue | 13 (13%) | 21 (21%)
Increased ALT | 13 (13%) | 15 (15%)
Hypertension | 12 (12%) | 5 (5%)
Epistaxis | 11 (11%) | 6 (6%)
Dyspnea | 10 (10%) | 11 (11%)
Leukopenia | 10 (10%) | 26 (27%)
Rash | 10 (10%) | 17 (17%)

Infusion-Related Reactions

Infusion-related reactions in GPA/MPA Study 1 were defined as any adverse event occurring within 24 hours of an infusion and considered to be infusion-related by investigators. Among the 99 patients treated with RITUXAN, 12% experienced at least one infusion-related reaction, compared with 11% of the 98 patients in the cyclophosphamide group. Infusion-related reactions included cytokine release syndrome, flushing, throat irritation, and tremor. In the RITUXAN group, the proportion of patients experiencing an infusion-related reaction was 12%, 5%, 4%, and 1% following the first, second, third, and fourth infusions, respectively. Patients were pre-medicated with antihistamine and acetaminophen before each RITUXAN infusion and were on background oral corticosteroids which may have mitigated or masked an infusion-related reaction; however, there is insufficient evidence to determine whether premedication diminishes the frequency or severity of infusion-related reactions.

Infections

In GPA/MPA Study 1, 62% (61/99) of patients in the RITUXAN group experienced an infection of any type compared to 47% (46/98) patients in the cyclophosphamide group by Month 6. The most common infections in the RITUXAN group were upper respiratory tract infections, urinary tract infections, and herpes zoster.

The incidence of serious infections was 11% in the RITUXAN-treated patients and 10% in the cyclophosphamide treated patients, with rates of approximately 25 and 28 per 100 patient-years, respectively. The most common serious infection was pneumonia.

Hypogammaglobulinemia

Hypogammaglobulinemia (IgA, IgG or IgM below the lower limit of normal) has been observed in patients with GPA and MPA treated with RITUXAN in GPA/MPA Study 1. At 6 months, in the RITUXAN group, 27%, 58% and 51% of patients with normal immunoglobulin levels at baseline, had low IgA, IgG and IgM levels, respectively compared to 25%, 50% and 46% in the cyclophosphamide group.

Follow up Treatment of Adult Patients with GPA/MPA who have Achieved Disease Control with Induction Treatment (GPA/MPA Study 2)

In GPA/MPA Study 2 (NCT00748644), an open-label, controlled, clinical study [See Clinical Studies (14.7)], evaluating the efficacy and safety of non-U.S.-licensed rituximab versus azathioprine as follow up treatment in adult patients with GPA, MPA or renal-limited ANCA-associated vasculitis who had achieved disease control after induction treatment with cyclophosphamide, a total of 57 GPA and MPA patients in disease remission received follow up treatment with two 500 mg intravenous infusions of non-U.S.-licensed rituximab, separated by two weeks on Day 1 and Day 15, followed by a 500 mg intravenous infusion every 6 months for 18 months.

The safety profile was consistent with the safety profile for RITUXAN in RA and GPA and MPA.

Infusion-Related Reactions

In GPA/MPA Study 2, 7/57 (12%) patients in the non-U.S.-licensed rituximab arm reported infusion-related reactions. The incidence of IRR symptoms was highest during or after the first infusion (9%) and decreased with subsequent infusions (less than 4%). One patient had two serious IRRs, two IRRs led to a dose modification, and no IRRs were severe, fatal, or led to withdrawal from the study.

Infections

In GPA/MPA Study 2, 30/57 (53%) patients in the non-U.S.-licensed rituximab arm and 33/58 (57%) in the azathioprine arm reported infections. The incidence of all grade infections was similar between the arms. The incidence of serious infections was similar in both arms (12%). The most commonly reported serious infection in the group was mild or moderate bronchitis.

Long-term, Observational Study with RITUXAN in Patients with GPA/MPA (GPA/MPA Study 3)

In a long-term observational safety study (NCT01613599), 97 patients with GPA or MPA received treatment with RITUXAN (mean of 8 infusions [range 1-28]) for up to 4 years, according to physician standard practice and discretion. Majority of patients received doses ranging from 500 mg to 1,000 mg, approximately every 6 months. The safety profile was consistent with the safety profile for RITUXAN in RA and GPA and MPA.

Treatment of Pediatric Patients with GPA/MPA (GPA/MPA Study 4)

An open-label, single arm study (NCT01750697) was conducted in 25 pediatric patients 6 years to 17 years of age with active GPA or MPA. The overall study period consisted of a 6-month remission induction phase and a minimum 12-month follow-up phase, up to 54 months. During the remission induction phase, patients received RITUXAN or non-U.S.-licensed rituximab. During the follow-up phase, RITUXAN or non-U.S.-licensed rituximab were given at the discretion of the investigator (17 out of 25 patients received this additional treatment). Concomitant treatment with other immunosuppressive therapy was permitted [see Clinical Studies (14.7)].

The safety profile in pediatric GPA and MPA patients was consistent in type, nature and severity with the known safety profile of RITUXAN in adult patients with RA, GPA and MPA, and PV.

Infusion-Related Reactions

In GPA/MPA Study 4, the proportion of patients experiencing an IRR was 32%, 20%, 12%, and 8% following the first, second, third, and fourth infusions, respectively. The observed symptoms of IRRs were similar to those in adult GPA and MPA patients treated with RITUXAN. [see Warning and Precautions (5.1)].

Serious Infections

Serious infections were reported in 7 patients (28%), and included influenza (2 patients [8%]) and lower respiratory tract infection (2 patients [8%]) as the most frequently reported events.

Hypogammaglobulinemia

Hypogammaglobulinemia (IgG or IgM below the lower limit of normal), including prolonged hypogammaglobulinemia (defined as Ig levels below lower limit of normal for at least 4 months) was observed in GPA/MPA Study 4. During the overall study period, 18/25 patients (72%) had prolonged low IgG levels, including 15 patients who also had prolonged low IgM. Three patients received treatment with intravenous immunoglobulin.

Pemphigus Vulgaris (PV)

PV Study 1

PV Study 1 (NCT00784589), a randomized, controlled, multicenter open-label study, evaluated the efficacy and safety of non-U.S.-licensed rituximab in combination with short-term prednisone compared to prednisone monotherapy in 90 patients (74 Pemphigus Vulgaris [PV] patients and 16 Pemphigus Foliaceus [PF] patients) [see Clinical Studies (14.8)]. Safety results for the PV patient population during the 24-month treatment period are described below.

The safety profile of the non-U.S.-licensed rituximab in patients with PV was consistent with that observed in patients with RITUXAN-treated RA and GPA and MPA [see Adverse Reactions (6.1)].

Adverse reactions from PV Study 1 are presented below in Table 6 and were adverse events which occurred at a rate greater than or equal to 5% among PV patients treated with non-U.S.-licensed rituximab and with at least 2% absolute difference in incidence between the group treated with non-U.S.-licensed rituximab and the prednisone monotherapy group up to Month 24. No patients in the group treated with non-U.S.-licensed rituximab withdrew due to adverse reactions. The clinical study did not include sufficient number of patients to allow for direct comparison of adverse reaction rates between treatment groups.

Table 6 Incidence of All Adverse Reactions Occurring in greater than or equal to 5% Among PV Patients Treated with Non-U.S.-licensed Rituximab and with at Least 2% Absolute Difference in Incidence Between the Group Treated with Non-U.S.-licensed Rituximab with Short-term Prednisone and the Group Treated with Prednisone Monotherapy in PV Study 1 (Up to Month 24)
Adverse Reaction | Non-U.S.-licensed rituximab + short-term prednisone N=38 n (%) | Prednisone N=36 n (%)
Infusion-related reactions [Infusion-related reactions included symptoms collected on the next scheduled visit after each infusion, and adverse reactions occurring on the day of or one day after the infusion. The most common infusion-related reactions included headaches, chills, high blood pressure, nausea, asthenia, and pain.] | 22 (58%) | N/A
Depression | 7 (18%) | 4 (11%)
Herpes simplex | 5 (13%) | 1 (3%)
Alopecia | 5 (13%) | 0 (0%)
Fatigue | 3 (8%) | 2 (6%)
Abdominal pain upper | 2 (5%) | 1 (3%)
Conjunctivitis | 2 (5%) | 0 (0%)
Dizziness | 2 (5%) | 0 (0%)
Headache | 2 (5%) | 1 (3%)
Herpes zoster | 2 (5%) | 1 (3%)
Irritability | 2 (5%) | 0 (0%)
Musculoskeletal pain | 2 (5%) | 0 (0%)
Pruritus | 2 (5%) | 0 (0%)
Pyrexia | 2 (5%) | 0 (0%)
Skin disorder | 2 (5%) | 0 (0%)
Skin papilloma | 2 (5%) | 0 (0%)
Tachycardia | 2 (5%) | 0 (0%)
Urticaria | 2 (5%) | 0 (0%)
N/A = not applicable

Infusion-Related Reactions

Infusion-related reactions were the most commonly reported adverse drug reactions (58%, 22 patients). All infusion-related reactions were mild to moderate (Grade 1 or 2) except one Grade 3 serious infusion-related reaction (arthralgia) associated with the Month 12 maintenance infusion. The proportion of patients experiencing an infusion-related reaction was 29% (11 patients), 40% (15 patients), 13% (5 patients), and 10% (4 patients) following the first, second, third, and fourth infusions, respectively. No patients were withdrawn from treatment due to infusion-related reactions. Symptoms of infusion-related reactions were similar in type and severity to those seen in RA and GPA and MPA patients [see Adverse Reactions (6.1)].

Infections

Fourteen patients (37%) in the group treated with non-U.S.-licensed rituximab experienced treatment-related infections compared to 15 patients (42%) in the prednisone group. The most common infections in the group treated with non-U.S.-licensed rituximab were herpes simplex, herpes zoster, bronchitis, urinary tract infection, fungal infection, and conjunctivitis. Three patients (8%) in the group treated with non-U.S.-licensed rituximab experienced a total of 5 serious infections (Pneumocystis jirovecii pneumonia, infective thrombosis, intervertebral discitis, lung infection, Staphylococcal sepsis) and 1 patient (3%) in the prednisone group experienced 1 serious infection (Pneumocystis jirovecii pneumonia).

PV Study 2

In PV Study 2 (NCT02383589), a randomized, double-blind, double-dummy, active-comparator, multicenter study evaluating the efficacy and safety of RITUXAN compared to mycophenolate mofetil (MMF) in patients with moderate-to-severe PV requiring oral corticosteroids, 67 PV patients received treatment with RITUXAN (initial 1,000 mg IV on Study Day 1 and a second 1,000 mg IV on Study Day 15 repeated at Weeks 24 and 26) for up to 52 weeks [see Clinical Studies (14.8)].

In PV Study 2, ADR defined as adverse events occurring in greater than or equal to 5% of patients in the RITUXAN arms and assessed as related are shown in Table 7.

Table 7 Incidence of All Adverse Reactions occurring in greater than or equal to 5% of RITUXAN-treated Pemphigus Vulgaris Patients (N=67) from PV Study 2 (up to Week 52)
Adverse Reactions | RITUXAN (N=67)
Infusion-related reactions | 15 (22%) [The most common infusion-related reaction symptoms/Preferred Terms for PV Study 2 in the RITUXAN arm were dyspnoea, erythema, hyperhidrosis, flushing/hot flush, hypotension/low blood pressure and rash/rash pruritic]
Upper respiratory tract infection/ Nasopharyngitis | 11 (16%)
Headache | 10 (15%)
Asthenia/Fatigue | 9 (13%)
Oral candidiasis | 6 (9%)
Arthralgia | 6 (9%)
Back pain | 6 (9%)
Urinary tract infection | 5 (8%)
Dizziness | 4 (6%)

Infusion-Related Reactions

In PV Study 2, IRRs occurred primarily at the first infusion and the frequency of IRRs decreased with subsequent infusions: 17.9%, 4.7%, 3.5% and 3.5% of patients experienced IRRs at the first, second, third, and fourth infusions, respectively. In 11/15 patients who experienced at least one IRR, the IRRs were Grade 1 or 2. In 4/15 patients, Grade greater than or equal to 3 IRRs were reported and led to discontinuation of RITUXAN treatment; three of the four patients experienced serious [life-threatening] IRRs. Serious IRRs occurred at the first (2 patients) or second (1 patient) infusion and resolved with symptomatic treatment.

Infections

In PV Study 2, 42/67 patients (62.7%) in the RITUXAN arm experienced infections. The most common infections in the RITUXAN arm were upper respiratory tract infection, nasopharyngitis, oral candidiasis and urinary tract infection. Six patients (9%) in the RITUXAN arm experienced serious infections.

Laboratory Abnormalities

In PV Study 2, in the RITUXAN arm, transient decreases in T-cell lymphocytes and phosphorus level were very commonly observed post-infusion. In some cases, treatment of hypophosphatemia was required.

Hypogammaglobulinemia (IgG or IgM below the lower limit of normal), including prolonged hypogammaglobulinemia (defined as Ig levels below lower limit of normal for at least 4 months) was observed in PV Study 2. Based on levels less than LLN measured at Week 16, Week 24, Week 40, and Week 52, 16.4% (11/67) of patients with normal baseline immunoglobulins had prolonged hypogammaglobulinemia (10 patients – IgM, 1 patient – both IgG and IgM) after treatment with RITUXAN.

6.2 Immunogenicity

As with all therapeutic proteins, there is a potential for immunogenicity. The detection of antibody formation is highly dependent on the sensitivity and specificity of the assay. Additionally, the observed incidence of antibody (including neutralizing antibody) positivity in an assay may be influenced by several factors including assay methodology, sample handling, timing of sample collection, concomitant medications, and underlying disease. For these reasons, comparison of the incidence of antibodies in the studies described below with the incidence of antibodies in other studies or to other rituximab products may be misleading.

Using an ELISA assay, anti-rituximab antibody was detected in 4 of 356 (1.1%) patients with low-grade or follicular NHL receiving single-agent RITUXAN. Three of the four patients had an objective clinical response.

A total of 273/2578 (11%) patients with RA tested positive for anti-rituximab antibodies at any time after receiving RITUXAN. Anti-rituximab antibody positivity was not associated with increased rates of infusion-related reactions or other adverse events. Upon further treatment, the proportions of patients with infusion-related reactions were similar between anti-rituximab antibody positive and negative patients, and most reactions were mild to moderate. Four anti-rituximab antibody positive patients had serious infusion-related reactions, and the temporal relationship between anti-rituximab antibody positivity and infusion-related reaction was variable.

A total of 23/99 (23%) RITUXAN-treated adult patients with GPA and MPA developed anti-rituximab antibodies by 18 months in GPA/MPA Study 1. The clinical relevance of anti-rituximab antibody formation in RITUXAN-treated adult patients is unclear. In GPA/MPA Study 4, a total of 4/21 (19%) RITUXAN-treated pediatric patients with GPA and MPA developed anti-rituximab antibodies during the overall study period (assessed at Month 18).

Using a new ELISA assay, a total of 19/34 (56%) patients with PV, who were treated with non-U.S.-licensed rituximab, tested positive for anti-rituximab antibodies by 18 months in PV Study 1. In PV Study 2, a total of 20/63 (32%) RITUXAN- treated PV patients tested positive for ADA by week 52 (19 patients had treatment-inducted ADA and 1 patient had treatment-enhanced ADA). The clinical relevance of anti-rituximab antibody formation in RITUXAN-treated PV patients is unclear.

6.3 Postmarketing Experience

The following adverse reactions have been identified during post-approval use of RITUXAN. Because these reactions are reported voluntarily from a population of uncertain size, it is not always possible to reliably estimate their frequency or establish a causal relationship to drug exposure.

- Hematologic: prolonged pancytopenia, marrow hypoplasia, Grade 3-4 prolonged or late-onset neutropenia, hyperviscosity syndrome in Waldenstrom's macroglobulinemia, prolonged hypogammaglobulinemia [see Warnings and Precautions (5.6)].
- Cardiac: fatal cardiac failure.
- Immune/Autoimmune Events: uveitis, optic neuritis, systemic vasculitis, pleuritis, lupus-like syndrome, serum sickness, polyarticular arthritis, and vasculitis with rash.
- Infection: viral infections, including progressive multifocal leukoencephalopathy (PML), increase in fatal infections in HIV-associated lymphoma, and a reported increased incidence of Grade 3 and 4 infections [see Warnings and Precautions (5.6)].
- Neoplasia: disease progression of Kaposi's sarcoma.
- Skin: severe mucocutaneous reactions, pyoderma gangrenosum (including genital presentation).
- Gastrointestinal: bowel obstruction and perforation.
- Pulmonary: fatal bronchiolitis obliterans and fatal interstitial lung disease.
- Nervous system: Posterior Reversible Encephalopathy Syndrome (PRES) / Reversible Posterior Leukoencephalopathy Syndrome (RPLS).

7 DRUG INTERACTIONS

Formal drug interaction studies have not been performed with RITUXAN. In patients with CLL, RITUXAN did not alter systemic exposure to fludarabine or cyclophosphamide. In clinical trials of patients with RA, concomitant administration of methotrexate or cyclophosphamide did not alter the pharmacokinetics of rituximab.

8 USE IN SPECIFIC POPULATIONS

8.1 Pregnancy

Risk Summary

Based on human data, RITUXAN can cause adverse developmental outcomes including B-cell lymphocytopenia in infants exposed to RITUXAN in-utero (see Clinical Considerations). In animal reproduction studies, intravenous administration of rituximab to pregnant cynomolgus monkeys during the period of organogenesis caused lymphoid B-cell depletion in the newborn offspring at doses resulting in 80% of the exposure (based on AUC) of those achieved following a dose of 2 grams in humans. Advise pregnant women of the risk to a fetus.

Adverse outcomes in pregnancy occur regardless of the health of the mother or the use of medications. The background risk of major birth defects and miscarriage for the indicated populations is unknown. The estimated background risk in the U.S. general population of major birth defects is 2%-4% and of miscarriage is 15%-20% of clinically recognized pregnancies.

Clinical Considerations

Fetal/Neonatal Adverse Reactions

Observe newborns and infants for signs of infection and manage accordingly.

Data

Human data

Postmarketing data indicate that B-cell lymphocytopenia generally lasting less than six months can occur in infants exposed to rituximab in-utero. Rituximab was detected postnatally in the serum of infants exposed in-utero.

Animal Data

An embryo-fetal developmental toxicity study was performed on pregnant cynomolgus monkeys. Pregnant animals received rituximab via the intravenous route during early gestation (organogenesis period; post coitum days 20 through 50). Rituximab was administered as loading doses on post coitum (PC) Days 20, 21 and 22, at 15, 37.5 or 75 mg/kg/day, and then weekly on PC Days 29, 36, 43 and 50, at 20, 50 or 100 mg/kg/week. The 100 mg/kg/week dose resulted in 80% of the exposure (based on AUC) of those achieved following a dose of 2 grams in humans. Rituximab crosses the monkey placenta. Exposed offspring did not exhibit any teratogenic effects but did have decreased lymphoid tissue B cells.

A subsequent pre-and postnatal reproductive toxicity study in cynomolgus monkeys was completed to assess developmental effects including the recovery of B cells and immune function in infants exposed to rituximab in utero. Animals were treated with a loading dose of 0, 15, or 75 mg/kg every day for 3 days, followed by weekly dosing with 0, 20, or 100 mg/kg dose. Subsets of pregnant females were treated from PC Day 20 through postpartum Day 78, PC Day 76 through PC Day 134, and from PC Day 132 through delivery and postpartum Day 28. Regardless of the timing of treatment, decreased B cells and immunosuppression were noted in the offspring of rituximab-treated pregnant animals. The B-cell counts returned to normal levels, and immunologic function was restored within 6 months postpartum.

8.2 Lactation

There are limited data on the presence of rituximab in human milk and the effect on the breastfed child, and there are no data on the effect on milk production. Rituximab is detected in the milk of lactating cynomolgus monkeys, and maternal IgG is present in human breast milk. Rituximab has also been reported to be excreted at low concentrations in human breast milk. Given that the clinical significance of this finding for children is not known, advise women not to breastfeed during treatment with RITUXAN and for 6 months after the last dose due to the potential of serious adverse reactions in breastfed children.

8.3 Females and Males of Reproductive Potential

RITUXAN can cause fetal harm when administered to a pregnant woman [see Use in Specific Populations (8.1)].

Pregnancy Testing

Verify pregnancy status in females of reproductive potential prior to initiating RITUXAN.

Contraception

Females

Advise females of reproductive potential to use effective contraception during treatment with RITUXAN and for 12 months after the last dose.

8.4 Pediatric Use

Granulomatosis with Polyangiitis (GPA) (Wegener's Granulomatosis) and Microscopic Polyangiitis (MPA)

RITUXAN is indicated for the treatment of GPA and MPA in pediatric patients 2 years of age and older with GPA and MPA. RITUXAN is not indicated in pediatric patients less than 2 years of age with GPA or MPA.

The use of RITUXAN for the treatment of pediatric patients with GPA and MPA 6 years of age and older is supported by evidence from adequate and well-controlled studies of RITUXAN in adults with GPA and MPA; a trial in pediatric patients 6 years of age and older with active GPA and MPA; and population pharmacokinetic (PK) analyses showing similar drug exposure levels in adults and pediatric patients 6 years to 17 years of age. The use of RITUXAN for the treatment of pediatric patients with GPA and MPA ages 2 to less than 6 years of age is supported by PK modeling in patients 2 years of age and older and safety data from pediatric patients less than 6 years of age treated with rituximab.

The pediatric trial was a multicenter, open-label, single arm study (GPA/MPA Study 4) to evaluate the safety, PK and exploratory efficacy of RITUXAN or non-U.S.-licensed rituximab in 25 pediatric patients (6 patients 6 years to less than 12 years of age and 19 patients 12 years to 17 years of age) with active GPA and MPA over a 6-month remission induction phase and minimum 12-month follow-up phase, up to 54 months [see Adverse Reactions (6.1), Clinical Pharmacology (12.3), and Clinical Studies (14.7)].

Mature B-Cell NHL/B-AL

The safety and effectiveness of RITUXAN in combination with chemotherapy for the treatment of previously untreated, advanced stage, CD20-positive DLBCL/BL/BLL/B-AL have been established in pediatric patients aged 6 months and older. Use of RITUXAN for this indication is supported by evidence from an adequate and well-controlled study in pediatric patients aged 1 year and older on the basis that the course of advanced disease is expected to be similar between pediatric patients aged 6 months to less than 1 year to that of pediatric patients aged 1 year and older to allow extrapolation of data to younger pediatric patients and use pharmacokinetic modeling [see Clinical Pharmacology (12.3), Clinical Studies (14.2)]. Patients younger than 3 years had a higher incidence of infections compared to patients 3 years and older [see Adverse Reactions (6.1)].

The safety and effectiveness of RITUXAN in combination with chemotherapy for previously untreated, advanced stage, CD20-positive DLBCL/BL/BLL/B-AL have not been established in pediatric patients less than 6 months of age.

The safety and effectiveness of RITUXAN have not been established in pediatric patients with CLL.

Rheumatoid Arthritis and Pemphigus Vulgaris

The safety and effectiveness of RITUXAN have not been established in pediatric patients with PV or RA.

RITUXAN was not studied in pediatric patients with polyarticular juvenile idiopathic arthritis (PJIA) due to concerns regarding the potential for prolonged immunosuppression as a result of B-cell depletion in the developing juvenile immune system.

8.5 Geriatric Use

Diffuse Large B-Cell NHL

Among patients with DLBCL evaluated in three randomized, active-controlled trials, 927 patients received RITUXAN in combination with chemotherapy. Of these, 396 (43%) were age 65 or greater and 123 (13%) were age 75 or greater. No overall differences in effectiveness were observed between these patients and younger patients. Cardiac adverse reactions, mostly supraventricular arrhythmias, occurred more frequently among elderly patients. Serious pulmonary adverse reactions were also more common among the elderly, including pneumonia and pneumonitis.

Low-Grade or Follicular Non-Hodgkin's Lymphoma

Patients with previously untreated follicular NHL evaluated in NHL Study 5 were randomized to RITUXAN as single-agent maintenance therapy (n=505) or observation (n=513) after achieving a response to RITUXAN in combination with chemotherapy. Of these, 123 (24%) patients in the RITUXAN arm were age 65 or older. No overall differences in safety or effectiveness were observed between these patients and younger patients. Other clinical studies of RITUXAN in low-grade or follicular, CD20-positive, B-cell NHL did not include sufficient numbers of patients aged 65 and over to determine whether they respond differently from younger subjects.

Chronic Lymphocytic Leukemia

Among patients with CLL evaluated in two randomized active-controlled trials, 243 of 676 RITUXAN-treated patients (36%) were 65 years of age or older; of these, 100 RITUXAN-treated patients (15%) were 70 years of age or older.

In exploratory analyses defined by age, there was no observed benefit from the addition of RITUXAN to fludarabine and cyclophosphamide among patients 70 years of age or older in CLL Study 1 or in CLL Study 2; there was also no observed benefit from the addition of RITUXAN to fludarabine and cyclophosphamide among patients 65 years of age or older in CLL Study 2 [see Clinical Studies (14.5)]. Patients 70 years or older received lower dose intensity of fludarabine and cyclophosphamide compared to younger patients, regardless of the addition of RITUXAN. In CLL Study 1, the dose intensity of RITUXAN was similar in older and younger patients, however in CLL Study 2 older patients received a lower dose intensity of RITUXAN.

The incidence of Grade 3 and 4 adverse reactions was higher among patients receiving R-FC who were 70 years or older compared to younger patients for neutropenia [44% vs. 31% (CLL Study 1); 56% vs. 39% (CLL Study 2)], febrile neutropenia [16% vs. 6% (NHL Study 10 (NCT00719472)], anemia [5% vs. 2% (CLL Study 1); 21% vs. 10% (CLL Study 2)], thrombocytopenia [19% vs. 8% (CLL Study 2)], pancytopenia [7% vs. 2% (CLL Study 1); 7% vs. 2% (CLL Study 2)] and infections [30% vs. 14% (CLL Study 2)].

Rheumatoid Arthritis

Among the 2578 patients in global RA studies completed to date, 12% were 65–75 years old and 2% were 75 years old and older. The incidences of adverse reactions were similar between older and younger patients. The rates of serious adverse reactions, including serious infections, malignancies, and cardiovascular events were higher in older patients.

Granulomatosis with Polyangiitis (GPA) (Wegener's Granulomatosis) and Microscopic Polyangiitis

Of the 99 RITUXAN-treated GPA and MPA patients in GPA/MPA Study 1, 36 (36%) were 65 years old and over, while 8 (8%) were 75 years and over. No overall differences in efficacy were observed between patients that were 65 years old and over and younger patients. The overall incidence and rate of all serious adverse events was higher in patients 65 years old and over. The clinical study did not include sufficient numbers of patients aged 65 and over to determine whether they respond differently from younger subjects.

In GPA/MPA Study 2, 30 (26%) of the enrolled patients were at least 65 years old, of which 12 patients were exposed to non-U.S.-licensed rituximab and 18 were exposed to azathioprine. The clinical study did not include sufficient numbers of patients aged 65 and over to determine whether they respond differently from younger subjects.

Pemphigus Vulgaris

Of the 46 patients treated with non-U.S.-licensed rituximab, 15 (33%) patients were 65 years of age and older. The clinical study did not include sufficient numbers of patients aged 65 and older to determine whether they respond differently from younger patients.

11 DESCRIPTION

Rituximab is a genetically engineered chimeric murine/human monoclonal IgG1 kappa antibody directed against the CD20 antigen. Rituximab has an approximate molecular weight of 145 kD.

Rituximab is produced by mammalian cell (Chinese Hamster Ovary) suspension culture in a nutrient medium that may contain the antibiotic gentamicin. Gentamicin is not detectable in the final product.

RITUXAN (rituximab) injection is a sterile, preservative-free, clear, colorless solution for intravenous infusion. RITUXAN is supplied at a concentration of 10 mg/mL in either 100 mg/10 mL or 500 mg/50 mL single-dose vials. Each mL of solution contains 10 mg rituximab, polysorbate 80 (0.7 mg), sodium chloride (9 mg), sodium citrate dihydrate (7.35 mg), and Water for Injection, USP. The pH is 6.5.

12 CLINICAL PHARMACOLOGY

12.1 Mechanism of Action

Rituximab is a monoclonal antibody that targets the CD20 antigen expressed on the surface of pre-B and mature B-lymphocytes. Upon binding to CD20, rituximab mediates B-cell lysis. Possible mechanisms of cell lysis include complement dependent cytotoxicity (CDC) and antibody dependent cell mediated cytotoxicity (ADCC). B cells are believed to play a role in the pathogenesis of rheumatoid arthritis (RA) and associated chronic synovitis. In this setting, B cells may be acting at multiple sites in the autoimmune/inflammatory process, including through production of rheumatoid factor (RF) and other autoantibodies, antigen presentation, T-cell activation, and/or proinflammatory cytokine production.

12.2 Pharmacodynamics

Non-Hodgkin's Lymphoma (NHL)

In NHL patients, administration of RITUXAN resulted in depletion of circulating and tissue-based B cells. Among 166 patients in NHL Study 1 (NCT000168740), circulating CD19-positive B cells were depleted within the first three weeks with sustained depletion for up to 6 to 9 months post treatment in 83% of patients. B-cell recovery began at approximately 6 months and median B-cell levels returned to normal by 12 months following completion of treatment.

There were sustained and statistically significant reductions in both IgM and IgG serum levels observed from 5 through 11 months following rituximab administration; 14% of patients had IgM and/or IgG serum levels below the normal range.

Rheumatoid Arthritis

In RA patients, treatment with RITUXAN induced depletion of peripheral B lymphocytes, with the majority of patients demonstrating near complete depletion (CD19 counts below the lower limit of quantification, 20 cells/µl) within 2 weeks after receiving the first dose of RITUXAN. The majority of patients showed peripheral B-cell depletion for at least 6 months. A small proportion of patients (~4%) had prolonged peripheral B-cell depletion lasting more than 3 years after a single course of treatment.

Total serum immunoglobulin levels, IgM, IgG, and IgA were reduced at 6 months with the greatest change observed in IgM. At Week 24 of the first course of RITUXAN treatment, small proportions of patients experienced decreases in IgM (10%), IgG (2.8%), and IgA (0.8%) levels below the lower limit of normal (LLN). In the experience with RITUXAN in RA patients during repeated RITUXAN treatment, 23.3%, 5.5%, and 0.5% of patients experienced decreases in IgM, IgG, and IgA concentrations below LLN at any time after receiving RITUXAN, respectively. The clinical consequences of decreases in immunoglobulin levels in RA patients treated with RITUXAN are unclear.

Treatment with rituximab in patients with RA was associated with reduction of certain biologic markers of inflammation such as interleukin-6 (IL-6), C-reactive protein (CRP), serum amyloid protein (SAA), S100 A8/S100 A9 heterodimer complex (S100 A8/9), anti-citrullinated peptide (anti-CCP), and RF.

Granulomatosis with Polyangiitis (GPA) (Wegener's Granulomatosis) and Microscopic Polyangiitis

In GPA and MPA patients in GPA/MPA Study 1, peripheral blood CD19 B-cells depleted to less than 10 cells/µl following the first two infusions of RITUXAN, and remained at that level in most (84%) patients through Month 6. By Month 12, the majority of patients (81%) showed signs of B-cell return with counts greater than 10 cells/µL. By Month 18, most patients (87%) had counts greater than 10 cells/µL.

In GPA/MPA Study 2 where patients received non-U.S.-licensed rituximab as two 500 mg intravenous infusions separated by two weeks, followed by a 500 mg intravenous infusion at Month 6, 12, and 18, 70% (30 out of 43) of the rituximab-treated patients with CD19+ peripheral B cells evaluated post-baseline had undetectable CD19+ peripheral B cells at Month 24. At Month 24, all 37 patients with evaluable baseline CD19+ peripheral B cells and Month 24 measurements had lower CD19+ B cells relative to baseline.

12.3 Pharmacokinetics

Non-Hodgkin's Lymphoma (NHL)

Pharmacokinetics were characterized in 203 NHL patients receiving 375 mg/m^2 RITUXAN weekly by intravenous infusion for 4 doses. Rituximab was detectable in the serum of patients 3 to 6 months after completion of treatment.

The pharmacokinetic profile of rituximab when administered as 6 infusions of 375 mg/m^2 in combination with 6 cycles of CHOP chemotherapy was similar to that seen with rituximab alone.

Based on a population pharmacokinetic analysis of data from 298 NHL patients who received rituximab once weekly or once every three weeks, the estimated median terminal elimination half-life was 22 days (range, 6.1 to 52 days). Patients with higher CD19-positive cell counts or larger measurable tumor lesions at pretreatment had a higher clearance. However, dose adjustment for pretreatment CD19 count or size of tumor lesion is not necessary. Age and gender had no effect on the pharmacokinetics of rituximab.

Pharmacokinetics were characterized in 21 patients with CLL receiving rituximab according to the recommended dose and schedule. The estimated median terminal half-life of rituximab was 32 days (range, 14 to 62 days).

Rheumatoid Arthritis

Following administration of 2 doses of RITUXAN in patients with RA, the mean (± S.D.; % CV) concentrations after the first infusion (Cmax first) and second infusion (Cmax second) were 157 (± 46; 29%) and 183 (± 55; 30%) mcg/mL, and 318 (± 86; 27%) and 381 (± 98; 26%) mcg/mL for the 2 × 500 mg and 2 × 1,000 mg doses, respectively.

Based on a population pharmacokinetic analysis of data from 2005 RA patients who received RITUXAN, the estimated clearance of rituximab was 0.335 L/day; volume of distribution was 3.1 L and mean terminal elimination half-life was 18.0 days (range, 5.17 to 77.5 days). Age, weight and gender had no effect on the pharmacokinetics of rituximab in RA patients.

Granulomatosis with Polyangiitis (GPA) (Wegener's Granulomatosis) and Microscopic Polyangiitis

The PK parameters in adult and pediatric patients 6 years to 17 years of age with GPA/MPA receiving 375 mg/m^2 intravenous RITUXAN or non-U.S.-licensed rituximab once weekly for four doses are summarized in Table 8.

Table 8 Population PK in pediatric patients (GPA/MPA Study 4) and adult patients (GPA/MPA Study 1) with GPA/MPA
Parameter | Statistic | Study
Parameter | Statistic | Pediatric GPA/MPA (GPA/MPA Study 4) | Adult GPA/MPA (GPA/MPA Study 1)
N | Number of Patients | 25 | 97
Terminal Half-life (days) | Median (Range) | 22 (11 to 42) | 25 (11 to 52)
AUC0-180d (µg/mL*day) | Median (Range) | 9787 (4838 to 20446) | 10302 (3653 to 21874)
Clearance (L/day) | Median (Range) | 0.222 (0.0996 to 0.381) | 0.279 (0.113 to 0.653)
Volume of Distribution (L) | Median (Range) | 2.28 (1.43 to 3.17) | 3.12 (2.42 to 3.91)

Based on a population PK analysis in pediatric patients with GPA and MPA, the PK parameters of rituximab were similar to those in adults with GPA and MPA, once taking into account the BSA effect on clearance and volume of distribution parameters. The population PK analysis in adults with GPA and MPA showed that male patients and patients with higher BSA or positive anti-rituximab antibody levels have higher clearance. However, further dose adjustment based on gender or anti-rituximab antibody status is not necessary.

Pemphigus Vulgaris

The PK parameters in adult PV patients receiving 1,000 mg IV infusion of RITUXAN at Days 1, 15, 168, and 182 are summarized in Table 9.

Table 9 Population PK in adult PV patients from PV Study 2
Parameter | Infusion Cycle
 | 1st cycle of 1,000 mg Day 1 and Day 15 N=67 | 2nd cycle of 1,000 mg Day 168 and Day 182 N=67
Terminal Half-life (days)
Median | 21.1 | 26.2
(Range) | (9.3 to 36.2) | (16.4 to 42.8)
Clearance (L/day)
Median | 0.30 | 0.24
(Range) | (0.16 to 1.51) | (0.13 to 0.45)
Central Volume of Distribution (L)
Median | 3.49 (2.48 to 5.22) | 3.49 (2.48 to 5.22)
(Range)

Following the first cycle of rituximab administration, the PK parameters of rituximab in patients with PV were similar to those in patients with RA and in patients with GPA/MPA. Following the 2nd cycle of rituximab administration, rituximab clearance decreased by 22% assuming Pemphigus Disease Area Index (PDAI) activity score of 0 at the start of both cycles, while the central volume of distribution remained unchanged. The presence of anti-rituximab antibodies was associated with a higher clearance resulting in lower rituximab concentrations.

Specific Populations

The clearance and volume of distribution of rituximab increased with increasing body surface area (BSA).

No formal studies were conducted to examine the effects of either renal or hepatic impairment on the pharmacokinetics of rituximab.

Pediatric patients

The pharmacokinetics of rituximab have been studied in pediatric patients 6 years of age and older with active GPA and MPA (GPA/MPA Study 4). The effect of body surface area on the pharmacokinetics of rituximab was assessed in a population pharmacokinetic analysis which included 6 patients 6 years to less than 12 years of age and 19 patients 12 years to 17 years of age with GPA and MPA. BSA was a significant covariate on rituximab pharmacokinetics. The median AUC0-180d in patients 2 years to 5 years of age (BSA of 0.5 m^2) was estimated to be 10100 (µg/mL*day) and is comparable to that in adults. For follow up treatment of pediatric patients with GPA/MPA, the 250 mg/m^2 dose is estimated to provide pediatric GPA and MPA patients with exposure comparable to that observed in adults [see Use in Special Populations (8.4) and Clinical Studies (14.7)].

In the clinical trial studying pediatric patients with DLBCL/BL/BLL/B-AL (NHL Study 11), the PK of rituximab was studied in a subset of 35 patients aged 3 years and older. The PK was comparable between the two age groups (greater than or equal to 3 to less than 12 years vs. greater than or equal to 12 to less than 18 years) (Table 10). After two RITUXAN IV infusions of 375 mg/m^2 in each of the two induction cycles (cycle 1 and 2) followed by one RITUXAN IV infusion of 375 mg/m^2 in each of the consolidation cycles (cycle 3 and 4), the maximum concentration was highest after the fourth infusion (cycle 2). With this dosing regimen, trough concentrations were sustained. The PK characteristics of RITUXAN IV in pediatric patients aged 3 years and older with DLBCL/BL/BLL/B-AL were similar to what has been observed in adult NHL patients. No PK data are available in the greater than or equal to 6 months to less than 3 years age group [see Use in Special Populations (8.4) and Clinical Studies (14.2)].

Table 10: Observed PK Parameters following the RITUXAN IV Dosing Regimen in Pediatric DLBCL/BL/BLL/B-AL
Age group | Greater than or equal to 3 to less than 12 years | Greater than or equal to 12 to less than 18 years
Cmax (µg/mL) | 374 (292, 446) | 297 (242, 394)
Ctrough (µg/mL) | 61.4 (34.9, 126) | 39.5 (19.2, 93.2)
AUC0-inf (µg*day/mL) | 5040 (3380, 10400) | 5040 (2740, 6970)
T1/2 (days) | 25.7 (18.0, 31.0) | 26.3 (16.9, 31.9)
Results are presented as median (min – max); Cmax is at Cycle 2 after 4th infusion; Ctrough is at pre-dose Cycle 4; AUC 0-inf and T1/2 are at Cycle 4.

Drug Interaction Studies

Formal drug interaction studies have not been performed with RITUXAN.

13 NONCLINICAL TOXICOLOGY

13.1 Carcinogenesis, Mutagenesis, Impairment of Fertility

No long-term animal studies have been performed to establish the carcinogenic or mutagenic potential of RITUXAN or to determine potential effects on fertility in males or females.

14 CLINICAL STUDIES

14.1 Relapsed or Refractory, Low-Grade or Follicular, CD20-Positive, B-Cell NHL

The safety and effectiveness of RITUXAN in relapsed, refractory CD20+ NHL were demonstrated in 3 single-arm studies enrolling 296 patients.

NHL Study 1

A multicenter, open-label, single-arm study was conducted in 166 patients with relapsed or refractory, low-grade or follicular, B-cell NHL who received 375 mg/m^2 of RITUXAN given as an intravenous infusion weekly for 4 doses. Patients with tumor masses > 10 cm or with > 5,000 lymphocytes/µL in the peripheral blood were excluded from the study.

Results are summarized in Table 11. The median time to onset of response was 50 days. Disease-related signs and symptoms (including B-symptoms) resolved in 64% (25/39) of those patients with such symptoms at study entry.

NHL Study 2

In a multicenter, single-arm study, 37 patients with relapsed or refractory, low-grade NHL received 375 mg/m^2 of RITUXAN weekly for 8 doses. Results are summarized in Table 11.

NHL Study 3

In a multicenter, single-arm study, 60 patients received 375 mg/m^2 of RITUXAN weekly for 4 doses. All patients had relapsed or refractory, low-grade or follicular, B-cell NHL and had achieved an objective clinical response to RITUXAN administered 3.8–35.6 months (median 14.5 months) prior to retreatment with RITUXAN. Of these 60 patients, 5 received more than one additional course of RITUXAN. Results are summarized in Table 11.

Bulky Disease

In pooled data from studies 1 and 3, 39 patients with bulky (single lesion > 10 cm in diameter) and relapsed or refractory, low-grade NHL received RITUXAN 375 mg/m^2 weekly for 4 doses. Results are summarized in Table 11.

Table 11 Summary of RITUXAN Efficacy Data in NHL by Schedule and Clinical Setting
 | Study 1 Weekly × 4 N=166 | Study 2 Weekly × 8 N=37 | Study 1 and Study 3 Bulky disease, Weekly × 4 N=39 [Six of these patients are included in the first column. Thus, data from 296 intent-to-treat patients are provided in this table.] | Study 3 Retreatment, Weekly × 4 N=60
Overall Response Rate | 48% | 57% | 36% | 38%
Complete Response Rate | 6% | 14% | 3% | 10%
Median Duration of Response [Kaplan-Meier projected with observed range.] , ["+" indicates an ongoing response.] , [Duration of response: interval from the onset of response to disease progression.] | 11.2 | 13.4 | 6.9 | 15.0
(Months) [Range] | [1.9 to 42.1+] | [2.5 to 36.5+] | [2.8 to 25.0+] | [3.0 to 25.1+]

14.2 Previously Untreated, Low-Grade or Follicular, CD20-Positive, B-Cell NHL

The safety and effectiveness of RITUXAN in previously untreated, low-grade or follicular, CD20+ NHL were demonstrated in 3 randomized, controlled trials enrolling 1,662 patients.

NHL Study 4

A total of 322 patients with previously untreated follicular NHL were randomized (1:1) to receive up to eight 3-week cycles of CVP chemotherapy alone (CVP) or in combination with RITUXAN 375 mg/m^2 on Day 1 of each cycle (R-CVP) in an open-label, multicenter study. The main outcome measure of the study was progression-free survival (PFS) defined as the time from randomization to the first of progression, relapse, or death.

Twenty-six percent of the study population was >60 years of age, 99% had Stage III or IV disease, and 50% had an International Prognostic Index (IPI) score greater than or equal to 2. The results for PFS as determined by a blinded, independent assessment of progression are presented in Table 12. The point estimates may be influenced by the presence of informative censoring. The PFS results based on investigator assessment of progression were similar to those obtained by the independent review assessment.

Table 12 Efficacy Results in NHL Study 4
 | Study Arm
 | R-CVP N=162 | CVP N=160
Median PFS (years) [p < 0.0001, two-sided stratified log-rank test.] | 2.4 | 1.4
Hazard ratio (95% CI) [Estimates of Cox regression stratified by center.] | 0.44 (0.29, 0.65)

NHL Study 5

An open-label, multicenter, randomized (1:1) study was conducted in 1,018 patients with previously untreated follicular NHL who achieved a response (CR or PR) to RITUXAN in combination with chemotherapy. Patients were randomized to RITUXAN as single-agent maintenance therapy, 375 mg/m^2 every 8 weeks for up to 12 doses or to observation. RITUXAN was initiated at 8 weeks following completion of chemotherapy. The main outcome measure of the study was progression-free survival (PFS), defined as the time from randomization in the maintenance/observation phase to progression, relapse, or death, as determined by independent review.

Of the randomized patients, 40% were greater than or equal to 60 years of age, 70% had Stage IV disease, 96% had ECOG performance status (PS) 0–1, and 42% had FLIPI scores of 3–5. Prior to randomization to maintenance therapy, patients had received R-CHOP (75%), R-CVP (22%), or R-FCM (3%); 71% had a complete or unconfirmed complete response and 28% had a partial response.

PFS was longer in patients randomized to RITUXAN as single agent maintenance therapy (HR: 0.54, 95% CI: 0.42, 0.70). The PFS results based on investigator assessment of progression were similar to those obtained by the independent review assessment.

Figure 1

Kaplan-Meier Plot of IRC Assessed PFS in NHL Study 5

NHL Study 6

A total of 322 patients with previously untreated low-grade, B-cell NHL who did not progress after 6 or 8 cycles of CVP chemotherapy were enrolled in an open-label, multicenter, randomized trial. Patients were randomized (1:1) to receive RITUXAN, 375 mg/m^2 intravenous infusion, once weekly for 4 doses every 6 months for up to 16 doses or no further therapeutic intervention. The main outcome measure of the study was progression-free survival defined as the time from randomization to progression, relapse, or death. Thirty-seven percent of the study population was greater than 60 years of age, 99% had Stage III or IV disease, and 63% had an IPI score greater than or equal to 2.

There was a reduction in the risk of progression, relapse, or death (hazard ratio estimate in the range of 0.36 to 0.49) for patients randomized to RITUXAN as compared to those who received no additional treatment.

NHL Study 11

RITUXAN in combination with chemotherapy was evaluated in Inter-B-NHL Ritux 2010 (NCT01516580), a multicenter, open-label, randomized trial of patients with previously untreated, advanced stage, CD20-positive DLBCL/BL/BLL/B-AL aged 6 months and older. Advanced stage is defined as Stage III with elevated lactose dehydrogenase (LDH) level [LDH greater than twice the institutional upper limit of the adult normal values] or stage IV B-cell NHL or B-AL. LMB therapy was administered based on the clinical group classification of group B (stage III with high LDH and non-central nervous system (CNS) (Stage IV), group C1 (B-AL, CNS positive and cerebrospinal fluid (CSF) negative) and C3 (CSF positive).

Patients were randomized to Lymphome Malin B (LMB) chemotherapy (corticosteroids, vincristine, cyclophosphamide, high-dose methotrexate, cytarabine, doxorubicin, etoposide and triple drug [methotrexate/cytarabine/ corticosteroid] intrathecal therapy) alone or in combination with RITUXAN or non-U.S. licensed rituximab, administered as six infusions of RITUXAN IV at a dose of 375 mg/m^2 BSA (two doses during each of the two induction courses and one during each of the two consolidation courses) as per the LMB scheme [see Dosage and Administration (2.2)].

The trial was planned to enroll 600 patients with 1:1 randomization. The randomization was stopped early for efficacy after 362 patients had been enrolled (181 in each arm) according to the first planned interim analysis result. A total of 328 randomized patients, aged 6 months and older, were included in the efficacy analyses, of which one patient under 3 years of age received intravenous RITUXAN or non-U.S.-licensed rituximab in combination with LMB chemotherapy. Demographic and disease characteristics of the randomized trial population are displayed in Table 13:

Table 13: Demographics and Disease Characteristics of the Randomized Trial Population - ITT
 | RITUXAN + LMB Chemotherapy N = 164 | LMB Chemotherapy N = 164
Male | 82% | 84%
Female | 18% | 17%
Age (years)
Median (range) | 8 (2, 17) | 7 (1, 17)
Age group
6 months to less than 3 years | 0.6% | 4%
3 to less than 12 years | 71% | 71%
12 to less than 18 years | 29% | 25%
BSA (m^2)
Median (range) | 1.0 (0.6, 2.3) | 0.97 (0.5, 2.7)
Therapeutic group
Group B high-risk | 49% | 51%
Group C1 | 40% | 40%
Group C3 | 11% | 10%
Disease Type
B-AL | 37% | 34%
Burkitt or Burkitt-like NHL | 55% | 56%
DLBCL | 8% | 8%
Bone marrow involvement | 45% | 45%
CNS involvement | 27% | 27%
BSA= Body Surface Area, B-AL=B-Cell Acute Leukemia, DLBCL= Diffuse Large B-cell Lymphoma, NHL= Non-Hodgkin's Lymphoma , CNS= Central Nervous System

Efficacy was established based on event-free survival (EFS), where an event was defined as occurrence of progressive disease, relapse, second malignancy, death from any cause, or non-response as evidenced by detection of viable cells in residue after the second CYVE course, whichever occurs first.

Efficacy analyses were performed in 328 randomized patients with a median follow-up of 3.1 years. The results are described in Table 14.

Table 14: Overview of Efficacy Results (ITT population)
Analysis | LMB (N = 164) | R-LMB (N=164)
EFS [Event-free survival rate was calculated based on 38 event.] | 28 events | 10 events
 | Two-sided unstratified log-rank test p-value 0.0012 [two-sided unstratified log-rank test, testing null hypothesis of equality of event-free survivorship in randomization arms R-LMB and LMB against alternative hypothesis "event-free survivorship in group R-LMB is higher than in LMB." The analysis was based on 53% of information where the p-value boundary was 0.014.]
 | Adjusted Cox HR [R-LMB Versus LMB] 0.32 (90% CI: 0.17, 0.58)
CI = confidence interval; EFS = event-free survival; HR = hazard ratio; ITT = intent-to-treat

As of data cutoff date of 31 December 2017, there were 20 and 8 deaths reported in LMB arm and R-LMB arm, respectively, with an estimated overall survival (OS) HR of 0.36 (95% CI, 0.16 - 0.81). No formal statistical test was conducted for overall survival and therefore the OS result is considered descriptive.

14.3 Diffuse Large B-Cell NHL (DLBCL)

The safety and effectiveness of RITUXAN were evaluated in three randomized, active-controlled, open-label, multicenter studies with a collective enrollment of 1854 patients. Patients with previously untreated diffuse large B-cell NHL received RITUXAN in combination with cyclophosphamide, doxorubicin, vincristine, and prednisone (CHOP) or other anthracycline-based chemotherapy regimens.

NHL Study 7

A total of 632 patients age greater than or equal to 60 years with DLBCL (including primary mediastinal B-cell lymphoma) were randomized in a 1:1 ratio to treatment with CHOP or R-CHOP. Patients received 6 or 8 cycles of CHOP, each cycle lasting 21 days. All patients in the R-CHOP arm received 4 doses of RITUXAN 375 mg/m^2 on Days –7 and –3 (prior to Cycle 1) and 48–72 hours prior to Cycles 3 and 5. Patients who received 8 cycles of CHOP also received RITUXAN prior to Cycle 7. The main outcome measure of the study was progression-free survival, defined as the time from randomization to the first of progression, relapse, or death. Responding patients underwent a second randomization to receive RITUXAN or no further therapy.

Among all enrolled patients, 62% had centrally confirmed DLBCL histology, 73% had Stage III–IV disease, 56% had IPI scores greater than or equal to 2, 86% had ECOG performance status of < 2, 57% had elevated LDH levels, and 30% had two or more extranodal disease sites involved. Efficacy results are presented in Table 15. These results reflect a statistical approach which allows for an evaluation of RITUXAN administered in the induction setting that excludes any potential impact of RITUXAN given after the second randomization.

Analysis of results after the second randomization in NHL Study 7 demonstrates that for patients randomized to R-CHOP, additional RITUXAN exposure beyond induction was not associated with further improvements in progression-free survival or overall survival.

NHL Study 8

A total of 399 patients with DLBCL, age greater than or equal to 60 years, were randomized in a 1:1 ratio to receive CHOP or R-CHOP. All patients received up to eight 3-week cycles of CHOP induction; patients in the R-CHOP arm received RITUXAN 375 mg/m^2 on Day 1 of each cycle. The main outcome measure of the study was event-free survival, defined as the time from randomization to relapse, progression, change in therapy, or death from any cause. Among all enrolled patients, 80% had Stage III or IV disease, 60% of patients had an age-adjusted IPI greater than or equal to 2, 80% had ECOG performance status scores less than 2, 66% had elevated LDH levels, and 52% had extranodal involvement in at least two sites. Efficacy results are presented in Table 15.

NHL Study 9

A total of 823 patients with DLBCL, aged 18–60 years, were randomized in a 1:1 ratio to receive an anthracycline-containing chemotherapy regimen alone or in combination with RITUXAN. The main outcome measure of the study was time to treatment failure, defined as time from randomization to the earliest of progressive disease, failure to achieve a complete response, relapse, or death. Among all enrolled patients, 28% had Stage III–IV disease, 100% had IPI scores of less than or equal to 1, 99% had ECOG performance status of < 2, 29% had elevated LDH levels, 49% had bulky disease, and 34% had extranodal involvement. Efficacy results are presented in Table 15.

Table 15 Efficacy Results in NHL Studies 7, 8, and 9
 | Study 7 (n = 632) |  |  | Study 8 (n = 399) |  |  | Study 9 (n = 823)
 | R-CHOP | CHOP |  | R-CHOP | CHOP |  | R-Chemo | Chemo
Main outcome | Progression-free survival (years) |  |  | Event-free survival (years) |  |  | Time to treatment failure (years)
Median of main outcome measure | 3.1 | 1.6 |  | 2.9 | 1.1 |  | NE [NE = Not reliably estimable.] | NE
Hazard ratio [R-CHOP vs. CHOP.] | 0.69 [Significant at p < 0.05, 2-sided.] |  |  | 0.60 |  |  | 0.45
Overall survival at 2 years [Kaplan-Meier estimates.] | 74% | 63% |  | 69% | 58% |  | 95% | 86%
Hazard ratio | 0.72 |  |  | 0.68 |  |  | 0.40

In NHL Study 8, overall survival estimates at 5 years were 58% vs. 46% for R-CHOP and CHOP, respectively.

14.4 Ninety-Minute Infusions in Previously Untreated Follicular NHL and DLBCL

In NHL Study 10, a total of 363 patients with previously untreated follicular NHL (n=113) or DLBCL (n=250) were evaluated in a prospective, open-label, multi-center, single-arm trial for the safety of 90-minute rituximab infusions. Patients with follicular NHL received rituximab 375 mg/m^2 plus CVP chemotherapy. Patients with DLBCL received rituximab 375 mg/m^2 plus CHOP chemotherapy. Patients with clinically significant cardiovascular disease were excluded from the study. Patients were eligible for a 90-minute infusion at Cycle 2 if they did not experience a Grade 3-4 infusion-related adverse event with Cycle 1 and had a circulating lymphocyte count less than or equal to 5,000/mm^3 before Cycle 2. All patients were pre-medicated with acetaminophen and an antihistamine and received the glucocorticoid component of their chemotherapy prior to RITUXAN infusion. The main outcome measure was the development of Grade 3-4 infusion-related reactions on the day of, or day after, the 90-minute infusion at Cycle 2 [see Adverse Reactions (6.1)].

Eligible patients received their Cycle 2 rituximab infusion over 90 minutes as follows: 20% of the total dose given in the first 30 minutes and the remaining 80% of the total dose given over the next 60 minutes [see Dosage and Administration (2.1)]. Patients who tolerated the 90-minute rituximab infusion at Cycle 2 continued to receive subsequent rituximab infusions at the 90-minute infusion rate for the remainder of the treatment regimen (through Cycle 6 or Cycle 8).

The incidence of Grade 3-4 infusion-related reactions at Cycle 2 was 1.1% (95% CI [0.3%, 2.8%]) among all patients, 3.5% (95% CI [1.0%, 8.8%]) for those patients treated with R-CVP, and 0.0% (95% CI [0.0%, 1.5%]) for those patients treated with R-CHOP. For Cycles 2-8, the incidence of Grade 3-4 infusion-related reactions was 2.8% (95% CI [1.3%, 5.0%]). No acute fatal infusion-related reactions were observed.

14.5 Chronic Lymphocytic Leukemia (CLL)

The safety and effectiveness of RITUXAN were evaluated in two randomized (1:1) multicenter open-label studies comparing FC alone or in combination with RITUXAN for up to 6 cycles in patients with previously untreated CLL [CLL Study 1 (n=817)] or previously treated CLL [CLL Study 2 (n=552)]. Patients received fludarabine 25 mg/m^2/day and cyclophosphamide 250 mg/m^2/day on days 1, 2 and 3 of each cycle, with or without RITUXAN. In both studies, seventy-one percent of CLL patients received 6 cycles and 90% received at least 3 cycles of RITUXAN-based therapy.

In CLL Study 1, 30% of patients were 65 years or older, 31% were Binet stage C, 45% had B symptoms, more than 99% had ECOG performance status (PS) 0–1, 74% were male, and 100% were White. In CLL Study 2, 44% of patients were 65 years or older, 28% had B symptoms, 82% received a prior alkylating drug, 18% received prior fludarabine, 100% had ECOG PS 0–1, 67% were male and 98% were White.

The main outcome measure in both studies was progression-free survival (PFS), defined as the time from randomization to progression, relapse, or death, as determined by investigators (CLL Study 1) or an independent review committee (CLL Study 2). The investigator assessed results in CLL Study 2 were supportive of those obtained by the independent review committee. Efficacy results are presented in Table 16.

Table 16 Efficacy Results in CLL Studies 1 and 2
 | Study 1 [As defined in 1996 National Cancer Institute Working Group guidelines.] (Previously untreated) |  | Study 2 (Previously treated)
 | R-FC N = 408 | FC N = 409 | R-FC N = 276 | FC N = 276
Median PFS (months) | 39.8 | 31.5 | 26.7 | 21.7
Hazard ratio (95% CI) | 0.56 (0.43, 0.71) |  | 0.76 (0.6, 0.96)
P value (Log-Rank test) | < 0.01 |  | 0.02
Response rate (95% CI) | 86% (82, 89) | 73% (68, 77) | 54% (48, 60) | 45% (37, 51)

Across both studies, 243 of 676 RITUXAN-treated patients (36%) were 65 years of age or older and 100 RITUXAN-treated patients (15%) were 70 years of age or older. The results of exploratory subset analyses in elderly patients are presented in Table 17.

Table 17 Efficacy Results in CLL Studies 1 and 2 in Subgroups Defined by Age [From exploratory analyses.]
 | Study 1 |  | Study 2
Age subgroup | Number of Patients | Hazard Ratio for PFS (95% CI) | Number of Patients | Hazard Ratio for PFS (95% CI)
Age less than 65 yrs | 572 | 0.52 (0.39, 0.70) | 313 | 0.61 (0.45, 0.84)
Age greater than or equal to 65 yrs | 245 | 0.62 (0.39, 0.99) | 233 | 0.99 (0.70, 1.40)
Age less than 70 yrs | 736 | 0.51 (0.39, 0.67) | 438 | 0.67 (0.51, 0.87)
Age greater than or equal to 70 yrs | 81 | 1.17 (0.51, 2.66) | 108 | 1.22 (0.73, 2.04)

14.6 Rheumatoid Arthritis (RA)

Reducing the Signs and Symptoms: Initial and Re-Treatment Courses

The efficacy and safety of RITUXAN were evaluated in two randomized, double-blind, placebo-controlled studies of adult patients with moderately to severely active RA who had a prior inadequate response to at least one TNF inhibitor. Patients were 18 years of age or older, diagnosed with active RA according to American College of Rheumatology (ACR) criteria, and had at least 8 swollen and 8 tender joints.

In RA Study 1 (NCT00468546), patients were randomized to receive either RITUXAN 2 × 1,000 mg + MTX or placebo + MTX for 24 weeks. Further courses of RITUXAN 2 × 1,000 mg + MTX were administered in an open label extension study at a frequency determined by clinical evaluation, but no sooner than 16 weeks after the preceding course of RITUXAN. In addition to the intravenous premedication, glucocorticoids were administered orally on a tapering schedule from baseline through Day 14. The proportions of patients achieving ACR 20, 50, and 70 responses at Week 24 of the placebo-controlled period are shown in Table 18.

In RA Study 2 (NCT00266227), all patients received the first course of RITUXAN 2 × 1,000 mg + MTX. Patients who experienced ongoing disease activity were randomized to receive a second course of either RITUXAN 2 × 1,000 mg + MTX or placebo + MTX, the majority between Weeks 24–28. The proportions of patients achieving ACR 20, 50, and 70 responses at Week 24, before the re-treatment course, and at Week 48, after retreatment, are shown in Table 18.

Table 18 ACR Responses in RA Study 1 and RA Study 2 (Percent of Patients) (Modified Intent-to-Treat Population)
Inadequate Response to TNF Antagonists
Study 1 24 Week Placebo-Controlled (Week 24) |  |  |  |  | Study 2 Placebo-Controlled Retreatment (Week 24 and Week 48)
Response | Placebo + MTX n = 201 | RITUXAN + MTX n = 298 | Treatment Difference (RITUXAN – Placebo) [For RA Study 1, weighted difference stratified by region (US, rest of the world) and Rheumatoid Factor (RF) status (positive greater than 20 IU/mL, negative < 20 IU/mL) at baseline; For RA Study 2, weighted difference stratified by RF status at baseline and greater than or equal to 20% improvement from baseline in both SJC and TJC at Week 24 (Yes/No).] (95% CI) |  | Response | Placebo + MTX Retreatment n = 157 | RITUXAN + MTX Retreatment n = 318 | Treatment Difference (RITUXAN – Placebo) [In RA Study 2, all patients received a first course of RITUXAN 2 × 1,000 mg. Patients who experienced ongoing disease activity were randomized to receive a second course of either RITUXAN 2 × 1,000 mg + MTX or placebo + MTX at or after Week 24.] , [Since all patients received a first course of RITUXAN, no comparison between Placebo + MTX and RITUXAN + MTX is made at Week 24.] , (95% CI)
ACR20 |  |  |  |  | ACR20
Week 24 | 18% | 51% | 33% (26%, 41%) |  | Week 24 | 48% | 45% | NA
 |  |  |  |  | Week 48 | 45% | 54% | 11% (2%, 20%)
ACR50 |  |  |  |  | ACR50
Week 24 | 5% | 27% | 21% (15%, 27%) |  | Week 24 | 27% | 21% | NA
 |  |  |  |  | Week 48 | 26% | 29% | 4% (-4%, 13%)
ACR70 |  |  |  |  | ACR70
Week 24 | 1% | 12% | 11% (7%, 15%) |  | Week 24 | 11% | 8% | NA
 |  |  |  |  | Week 48 | 13% | 14% | 1% (-5%, 8%)

Improvement was also noted for all components of ACR response following treatment with RITUXAN, as shown in Table 19.

Table 19 Components of ACR Response at Week 24 in RA Study 1 (Modified Intent-to-Treat Population)
Inadequate Response to TNF Antagonists
Parameter (median) | Placebo + MTX (n = 201) |  | RITUXAN + MTX (n = 298)
Parameter (median) | Baseline | Wk 24 | Baseline | Wk 24
Tender Joint Count | 31.0 | 27.0 | 33.0 | 13.0
Swollen Joint Count | 20.0 | 19.0 | 21.0 | 9.5
Physician Global Assessment [Visual Analogue Scale: 0 = best, 100 = worst.] | 71.0 | 69.0 | 71.0 | 36.0
Patient Global Assessment | 73.0 | 68.0 | 71.0 | 41.0
Pain | 68.0 | 68.0 | 67.0 | 38.5
Disability Index (HAQ) [Disability Index of the Health Assessment Questionnaire: 0 = best, 3 = worst.] | 2.0 | 1.9 | 1.9 | 1.5
CRP (mg/dL) | 2.4 | 2.5 | 2.6 | 0.9

The time course of ACR 20 response for RA Study 1 is shown in Figure 2. Although both treatment groups received a brief course of intravenous and oral glucocorticoids, resulting in similar benefits at Week 4, higher ACR 20 responses were observed for the RITUXAN group by Week 8. A similar proportion of patients achieved these responses through Week 24 after a single course of treatment (2 infusions) with RITUXAN. Similar patterns were demonstrated for ACR 50 and 70 responses.

Figure 2

Percent of Patients Achieving ACR 20 Response by Visit [The same patients may not have responded at each time point.]
RA Study 1 (Inadequate Response to TNF Antagonists)

Radiographic Response

In RA Study 1, structural joint damage was assessed radiographically and expressed as changes in Genant-modified Total Sharp Score (TSS) and its components, the erosion score (ES) and the joint space narrowing (JSN) score. RITUXAN + MTX slowed the progression of structural damage compared to placebo + MTX after 1 year as shown in Table 20.

Table 20 Mean Radiographic Change From Baseline to 104 Weeks in RA Study 1
Inadequate Response to TNF Antagonists
Parameter | RITUXAN 2 × 1,000 mg + MTX [Patients received up to 2 years of treatment with RITUXAN + MTX.] | Placebo + MTX [Patients receiving Placebo + MTX. Patients receiving Placebo + MTX could have received retreatment with RITUXAN + MTX from Week 16 onward.] | Treatment Difference (Placebo – RITUXAN) | 95% CI
Change during First Year
TSS | 0.66 | 1.77 | 1.11 | (0.47, 1.75)
ES | 0.44 | 1.19 | 0.75 | (0.32, 1.19)
JSN Score | 0.22 | 0.58 | 0.36 | (0.10, 0.62)
Change during Second Year [Based on radiographic scoring following 104 weeks of observation.]
TSS | 0.48 | 1.04 | — | —
ES | 0.28 | 0.62 | — | —
JSN Score | 0.20 | 0.42 | — | —

In RA Study 1 and its open-label extension, 70% of patients initially randomized to RITUXAN + MTX and 72% of patients initially randomized to placebo + MTX were evaluated radiographically at Year 2. As shown in Table 20, progression of structural damage in RITUXAN + MTX patients was further reduced in the second year of treatment.

Following 2 years of treatment with RITUXAN + MTX, 57% of patients had no progression of structural damage. During the first year, 60% of RITUXAN + MTX treated patients had no progression, defined as a change in TSS of zero or less compared to baseline, compared to 46% of placebo + MTX treated patients. In their second year of treatment with RITUXAN + MTX, more patients had no progression than in the first year (68% vs. 60%), and 87% of the RITUXAN + MTX treated patients who had no progression in the first year also had no progression in the second year.

Lesser Efficacy of 500 Vs. 1,000 mg Treatment Courses for Radiographic Outcomes

RA Study 3 (NCT00299104) is a randomized, double-blind, placebo-controlled study which evaluated the effect of placebo + MTX compared to RITUXAN 2 × 500 mg + MTX and RITUXAN 2 × 1,000 mg + MTX treatment courses in MTX-naïve RA patients with moderately to severely active disease. Patients received a first course of two infusions of rituximab or placebo on Days 1 and 15. MTX was initiated at 7.5 mg/week and escalated up to 20 mg/week by Week 8 in all three treatment arms. After a minimum of 24 weeks, patients with ongoing disease activity were eligible to receive re-treatment with additional courses of their assigned treatment. After one year of treatment, the proportion of patients achieving ACR 20/50/70 responses were similar in both RITUXAN dose groups and were higher than in the placebo group. However, with respect to radiographic scores, only the RITUXAN 1,000 mg treatment group demonstrated a statistically significant reduction in TSS: a change of 0.36 units compared to 1.08 units for the placebo group, a 67% reduction.

Physical Function Response

RA Study 4 (NCT00299130) is a randomized, double-blind, placebo-controlled study in adult RA patients with moderately to severely active disease with inadequate response to MTX. Patients were randomized to receive an initial course of RITUXAN 500 mg, RITUXAN 1,000 mg, or placebo in addition to background MTX.

Physical function was assessed at Weeks 24 and 48 using the Health Assessment Questionnaire Disability Index (HAQ-DI). From baseline to Week 24, a greater proportion of RITUXAN-treated patients had an improvement in HAQ-DI of at least 0.22 (a minimal clinically important difference) and a greater mean HAQ-DI improvement compared to placebo, as shown in Table 21. HAQ-DI results for the RITUXAN 500 mg treatment group were similar to the RITUXAN 1,000 mg treatment group; however radiographic responses were not assessed (see Dosing Precaution in the Radiographic Responses section above). These improvements were maintained at 48 weeks.

Table 21 Improvement from Baseline in Health Assessment Questionnaire Disability Index (HAQ-DI) at Week 24 in RA Study 4
 | Placebo + MTX n = 172 | RITUXAN 2 × 1,000 mg + MTX n = 170 | Treatment Difference (RITUXAN – Placebo) [Adjusted difference stratified by region (US, rest of the world) and rheumatoid factor (RF) status (positive greater than or equal to 20 IU/mL, negative less than 20 IU/mL) at baseline.] (95% CI)
Mean Improvement from Baseline | 0.19 | 0.42 | 0.23 (0.11, 0.34)
Percent of patients with "Improved" score (Change from Baseline greater than or equal to MCID) [Minimal Clinically Important Difference: MCID for HAQ = 0.22.] | 48% | 58% | 11% (0%, 21%)

14.7 Granulomatosis with Polyangiitis (GPA) (Wegener's Granulomatosis) and Microscopic Polyangiitis (MPA)

Induction Treatment of Adult Patients with Active Disease (GPA/MPA Study 1)

A total of 197 patients with active, severe GPA and MPA (two forms of ANCA Associated Vasculitides) were treated in a randomized, double-blind, active-controlled, multicenter, non-inferiority study, conducted in two phases – a 6 month remission induction phase and a 12 month remission maintenance phase. Patients were 15 years of age or older, diagnosed with GPA (75% of patients) or MPA (24% of patients) according to the Chapel Hill Consensus conference criteria (1% of the patients had unknown vasculitis type). All patients had active disease, with a Birmingham Vasculitis Activity Score for Granulomatosis with Polyangiitis (BVAS/GPA) greater than or equal to 3, and their disease was severe, with at least one major item on the BVAS/GPA. Ninety-six (49%) of patients had new disease and 101 (51%) of patients had relapsing disease.

Patients in both arms received 1,000 mg of pulse intravenous methylprednisolone per day for 1 to 3 days within 14 days prior to initial infusion. Patients were randomized in a 1:1 ratio to receive either RITUXAN 375 mg/m^2 once weekly for 4 weeks or oral cyclophosphamide 2 mg/kg daily for 3 to 6 months in the remission induction phase. Patients were pre-medicated with antihistamine and acetaminophen prior to RITUXAN infusion. Following intravenous corticosteroid administration, all patients received oral prednisone (1 mg/kg/day, not exceeding 80 mg/day) with pre-specified tapering. Once remission was achieved or at the end of the 6 month remission induction period, the cyclophosphamide group received azathioprine to maintain remission. The RITUXAN group did not receive additional therapy to maintain remission. The main outcome measure for both GPA and MPA patients was achievement of complete remission at 6 months defined as a BVAS/GPA of 0, and off glucocorticoid therapy. The pre-specified non-inferiority margin was a treatment difference of 20%. As shown in Table 22, the study demonstrated non-inferiority of RITUXAN to cyclophosphamide for complete remission at 6 months.

Table 22 Percentage of Patients with GPA/MPA Who Achieved Complete Remission at 6 Months (Intent-to-Treat Population)
 | RITUXAN (n = 99) | Cyclophosphamide (n = 98) | Treatment Difference (RITUXAN – Cyclophosphamide)
Rate | 64% | 53% | 11%
95.1% [The 95.1% confidence level reflects an additional 0.001 alpha to account for an interim efficacy analysis.] CI | (54%, 73%) | (43%, 63%) | (-3%, 24%) [Non-inferiority was demonstrated because the lower bound was higher than the prespecified non-inferiority margin (-3% greater than -20%).]

Complete Remission (CR) at 12 and 18 months

In the RITUXAN group, 44% of patients achieved CR at 6 and 12 months, and 38% of patients achieved CR at 6, 12, and 18 months. In patients treated with cyclophosphamide (followed by azathioprine for maintenance of CR), 38% of patients achieved CR at 6 and 12 months, and 31% of patients achieved CR at 6, 12, and 18 months.

Retreatment of Flares with RITUXAN

Based upon investigator judgment, 15 patients received a second course of RITUXAN therapy for treatment of relapse of disease activity which occurred between 8 and 17 months after the induction treatment course of RITUXAN.

Follow up Treatment of Adult Patients with GPA/MPA who have achieved disease control with other Immunosuppressant (GPA/MPA Study 2)

A total of 115 patients (86 with GPA, 24 with MPA, and 5 with renal-limited ANCA-associated vasculitis) in disease remission were randomized to receive azathioprine (58 patients) or non-U.S.-licensed rituximab (57 patients) in this open-label, prospective, multi-center, randomized, active-controlled study. Eligible patients were 21 years and older and had either newly diagnosed (80%) or relapsing disease (20%). A majority of the patients were ANCA-positive. Remission of active disease was achieved using a combination of glucocorticoids and cyclophosphamide. Within a maximum of 1 month after the last cyclophosphamide dose, eligible patients (based on BVAS of 0), were randomized in a 1:1 ratio to receive either non-U.S.-licensed rituximab or azathioprine.

The non-U.S.-licensed rituximab was administered as two 500 mg intravenous infusions separated by two weeks (on Day 1 and Day 15) followed by a 500 mg intravenous infusion every 6 months for 18 months. Azathioprine was administered orally at a dose of 2 mg/kg/day for 12 months, then 1.5 mg/kg/day for 6 months, and finally 1 mg/kg/day for 4 months; treatment was discontinued after 22 months. Prednisone treatment was tapered and then kept at a low dose (approximately 5 mg per day) for at least 18 months after randomization. Prednisone dose tapering and the decision to stop prednisone treatment after month 18 were left at the investigator's discretion.

Planned follow-up was until month 28 (10 or 6 months, respectively, after the last non-U.S.-licensed rituximab infusion or azathioprine dose). The primary endpoint was the occurrence of major relapse (defined by the reappearance of clinical and/or laboratory signs of vasculitis activity that could lead to organ failure or damage, or could be life threatening) through month 28.

By month 28, major relapse occurred in 3 patients (5%) in the non-U.S.-licensed rituximab group and 17 patients (29%) in the azathioprine group.

The observed cumulative incidence rate of first major relapse during the 28 months was lower in patients on non-U.S.-licensed rituximab relative to azathioprine (Figure 3).

Figure 3
Cumulative Incidence Over Time of First Major Relapse in Patients with GPA/MPA

Patients were censored at the last follow-up dates if they had no event

Treatment of Pediatric Patients (GPA/MPA Study 4)

The study design consisted of an initial 6-month remission induction phase, and a minimum 12-month follow-up phase up to a maximum of 54 months (4.5 years) in pediatric patients 2 years to 17 years of age with GPA and MPA. Patients were to receive a minimum of 3 doses of intravenous methylprednisolone (30 mg/kg/day, not exceeding 1g/day) prior to the first RITUXAN or non-U.S.-licensed rituximab intravenous infusion. If clinically indicated, additional daily doses (up to three), of intravenous methylprednisolone could be given. The remission induction regimen consisted of four once weekly intravenous infusions of RITUXAN or non-U.S.-licensed rituximab at a dose of 375 mg/m^2 BSA, on study days 1, 8, 15 and 22 in combination with oral prednisolone or prednisone at 1 mg/kg/day (max 60 mg/day) tapered to 0.2 mg/kg/day minimum (max 10 mg/day) by Month 6. After the remission induction phase, patients could receive subsequent RITUXAN or non-U.S.-licensed rituximab intravenous infusions on or after Month 6 to maintain remission and control disease activity.

The primary objectives of this study were to evaluate safety and PK parameters in pediatric GPA and MPA patients (2 years to 17 years of age). The efficacy objectives of the study were exploratory and principally assessed using the Pediatric Vasculitis Activity Score (PVAS).

A total of 25 pediatric patients 6 years to 17 years of age with active GPA and MPA were treated with RITUXAN or non-U.S.-licensed rituximab in a multicenter, open-label, single-arm, uncontrolled study (NCT01750697). The median age of patients in the study was 14 years and the majority of patients (20/25 [80%]) were female. A total of 19 patients (76%) had GPA and 6 patients (24%) had MPA at baseline. Eighteen patients (72%) had newly diagnosed disease upon study entry (13 patients with GPA and 5 patients with MPA) and 7 patients had relapsing disease (6 patients with GPA and 1 patient with MPA).

All 25 patients completed all four once weekly intravenous infusions for the 6-month remission induction phase. A total of 24 out of 25 patients completed at least 18 months from Day 1 (baseline).

The exploratory efficacy using the PVAS is described in Table 23.

Table 23 Percentage of Patients Who Achieved PVAS Remission by Month 6, 12 and 18 (GPA/MPA Study 4)
 | Time to Follow Up Since Day 1
 | Month 6 n=25 | Month 12 n = 25 | Month 18 n = 25
Response rate | 56% | 92% | 100%
95% CI [The efficacy results are exploratory and no formal statistical testing was performed for these endpoints] | (34.9%, 75.6%) | (74.0%, 99.0%) | (86.3%, 100.0%)
*PVAS remission is defined by a PVAS of 0 and achieved glucocorticoid taper to 0.2 mg/kg/day (or 10 mg/day, whichever is lower), or a PVAS of 0 on two consecutive readings greater than or equal to 4 weeks apart irrespective of glucocorticoid dose

Follow-Up Treatment

After the 6-month remission induction phase, patients who had not achieved remission or who had progressive disease or flare that could not be controlled by glucocorticoids alone received additional treatment for GPA and MPA, that could include RITUXAN or non-U.S.-licensed rituximab and/or other therapies, at the discretion of the investigator. Planned follow-up was until Month 18 (from Day 1).

Fourteen out of 25 patients (56%) received additional RITUXAN or non-U.S.-licensed rituximab treatment at or post Month 6, up to Month 18. Five of these patients received four once weekly doses (375 mg/m^2) of intravenous RITUXAN or non-U.S.-licensed rituximab approximately every 6 months; 5 of these patients received a single dose (375 mg/m^2) of RITUXAN or non-U.S.-licensed rituximab every 6 months, and 4 of these patients received various other RITUXAN or non-U.S.-licensed rituximab doses/regimens according to investigator. Of the 14 patients who received follow-up treatment between Month 6 and Month 18, 4 patients first achieved remission between Months 6 and 12 and 1 patient first achieved remission between Months 12 and 18. Nine of these 14 patients achieved PVAS remission by Month 6 but required additional follow-up treatment after Month 6.

14.8 Pemphigus Vulgaris (PV)

PV Study 1 (NCT00784589)

Non-U.S.-licensed rituximab in combination with short-term prednisone was compared to prednisone monotherapy as first-line treatment in 90 newly diagnosed adult patients with moderate to severe pemphigus (74 Pemphigus Vulgaris [PV] and 16 Pemphigus Foliaceus [PF]) in this randomized, open-label, controlled, multicenter study (PV Study 1). Patients were between 19 and 79 years of age and had not received prior therapies for pemphigus. In the PV population, 5 (13%) patients in the group treated with non-U.S.-licensed rituximab and 3 (8%) patients in the prednisone group had moderate disease and 33 (87%) patients in the group treated with non-U.S.-licensed rituximab and 33 (92%) patients in the prednisone group had severe disease according to disease severity defined by Harman's criteria.

Patients were stratified by baseline disease severity (moderate or severe) and randomized 1:1 to receive either the non-U.S.-licensed rituximab and short-term prednisone or long-term prednisone monotherapy. Patients were pre-medicated with antihistamine, acetaminophen and methylprednisolone prior to infusion of the non-U.S.-licensed rituximab. Patients randomized to the group treated with non-U.S.-licensed rituximab received an initial intravenous infusion of 1,000 mg non-U.S.-licensed rituximab on Study Day 1 in combination with a short-term regimen of 0.5 mg/kg/day oral prednisone tapered off over 3 months if they had moderate disease or 1 mg/kg/day oral prednisone tapered off over 6 months if they had severe disease. All patients received a second intravenous infusion of 1,000 mg non-U.S.-licensed rituximab on Study Day 15. Maintenance infusions of 500 mg non-U.S.-licensed rituximab were administered at Months 12 and 18. Patients randomized to the prednisone monotherapy group received an initial 1 mg/kg/day oral prednisone tapered off over 12 months if they had moderate disease or 1.5 mg/kg/day oral prednisone tapered off over 18 months if they had severe disease. Patients in the group treated with non-U.S.-licensed rituximab who relapsed could receive an additional infusion of 1,000 mg non-U.S.-licensed rituximab in combination with reintroduced or escalated prednisone dose. Maintenance and relapse infusions were administered no sooner than 16 weeks following the previous infusion.

The primary endpoint for the study was complete remission (complete epithelialization and absence of new and/or established lesions) at Month 24 without the use of prednisone therapy for 2 months or more (CRoff for greater than or equal to 2 months).

The results of the trial are presented in Table 24.

Table 24 Percentage of Pemphigus Patients in Complete Remission Off Corticosteroid Therapy for Two Months or More (CRoff greater than or equal to 2 months) at Month 24, PV Study 1 (Intent-to-Treat Population)
 | Non-U.S.-licensed rituximab + short-term prednisone N=46 | Prednisone N=44
Number of responders (response rate [%]) | 41 (89%) | 15 (34%)
PV patients | 34/38 (90%) | 10/36 (28%)
PF patients | 7/8 (88%) | 5/8 (63%)

PV Study 2 (NCT02383589)

In a randomized, double-blind, double-dummy, active-comparator, multicenter study, the efficacy and safety of RITUXAN compared to mycophenolate mofetil (MMF) were evaluated in patients with moderate-to-severe PV receiving 60-120 mg/day oral prednisone or equivalent (1.0-1.5 mg/kg/day) at study entry and tapered to reach a dose of 60 or 80 mg/day by Day 1. Patients had a confirmed diagnosis of PV within the previous 24 months and evidence of moderate-to-severe disease defined as a total Pemphigus Disease Area Index (PDAI) activity score of greater than or equal to 15. The study consisted of a screening period of up to 28 days, a 52-week double-blind treatment period, and a 48-week safety follow up period.

One hundred and thirty-five patients were randomized to treatment with RITUXAN 1,000 mg administered on Day 1, Day 15, Week 24 and Week 26 or oral MMF 2 g/day (starting at 1 g/day on Day 1 and titrated to achieve a goal of 2 g/day by Week 2) for 52 weeks in combination with an initial dose of 60 or 80 mg oral prednisone with the aim of tapering to 0 mg/day by Week 24. Randomization was stratified by duration of PV (within the 1 year prior to screening or greater than 1 year) and geographical region. A dual-assessor approach was used during the study for efficacy and safety evaluations to prevent potential unblinding.

One hundred and twenty-five patients (excluding exploratory data from ten telemedicine patients) were analyzed for efficacy (Modified Intent-to-Treat Population). The primary efficacy endpoint for this study was the proportion of subjects achieving sustained complete remission defined as achieving healing of lesions with no new active lesions (i.e., PDAI activity score of 0) while on 0 mg/day prednisone or equivalent, and maintaining this response for at least 16 consecutive weeks, during the 52-week treatment period.

Secondary endpoints included cumulative oral corticosteroid dose and the total number of disease flares.

The results of the trial are presented in Table 25.

Table 25 Percentage of PV Patients Who Achieved Sustained Complete Remission Off Corticosteroid Therapy for 16 Weeks or More at Week 52 (Modified Intent-to-Treat Population)
 | RITUXAN (N=62) | MMF (N=63) | Difference (95% CI)
Number of responders (response rate [%]) | 25 (40.3%) | 6 (9.5%) | 30.80% (14.70%, 45.15%)
MMF = Mycophenolate mofetil. CI = Confidence Interval.

Glucocorticoid exposure

The median (min, max) cumulative oral prednisone dose at Week 52 was 2775 mg (450, 22180) in the RITUXAN group compared to 4005 mg (900, 19920) in the MMF group. Topical corticosteroid use and pre-infusion IV methylprednisolone were not included in this analysis. Prior to each infusion, the RITUXAN group received IV methylprednisolone 100 mg and the MMF group received IV saline solution.

Disease flare

Disease flare was defined as an appearance of 3 or more new lesions a month that do not heal spontaneously within 1 week or by the extension of established lesions in a patient who has achieved disease control. The total number of disease flares was lower in patients treated with RITUXAN compared to MMF (6 vs. 44).

16 HOW SUPPLIED/STORAGE AND HANDLING

RITUXAN (rituximab) injection is a sterile, preservative-free, clear, colorless solution for intravenous infusion supplied as follows:

Carton contents | NDC number
One 100 mg/10 mL (10 mg/mL) single-dose vial | NDC 50242-051-21
Ten 100 mg/10 mL (10 mg/mL) single-dose vials | NDC 50242-051-10
One 500 mg/50 mL (10 mg/mL) single-dose vial | NDC 50242-053-06

STORAGE AND HANDLING

Store RITUXAN vials refrigerated at 2°C to 8°C (36°F to 46°F). RITUXAN vials should be protected from direct sunlight. Do not freeze or shake.

17 PATIENT COUNSELING INFORMATION

Advise the patient to read the FDA-approved patient labeling (Medication Guide).

Infusion-Related Reactions

Inform patients about the signs and symptoms of infusion-related reactions. Advise patients to contact their healthcare provider immediately to report symptoms of infusion-related reactions including urticaria, hypotension, angioedema, sudden cough, breathing problems, weakness, dizziness, palpitations, or chest pain [see Warnings and Precautions (5.1)].

Severe Mucocutaneous Reactions

Advise patients to contact their healthcare provider immediately for symptoms of severe mucocutaneous reactions, including painful sores or ulcers on the mouth, blisters, peeling skin, rash, and pustules [see Warnings and Precautions (5.2)].

Hepatitis B Virus Reactivation

Advise patients to contact their healthcare provider immediately for symptoms of hepatitis including worsening fatigue or yellow discoloration of skin or eyes [see Warnings and Precautions (5.3)].

Progressive Multifocal Leukoencephalopathy (PML)

Advise patients to contact their healthcare provider immediately for signs and symptoms of PML, including new or changes in neurological symptoms such as confusion, dizziness or loss of balance, difficulty talking or walking, decreased strength or weakness on one side of the body, or vision problems [see Warnings and Precautions (5.4)].

Tumor Lysis Syndrome (TLS)

Advise patients to contact their healthcare provider immediately for signs and symptoms of tumor lysis syndrome such as nausea, vomiting, diarrhea, and lethargy [see Warnings and Precautions (5.5)].

Infections

Advise patients to contact their healthcare provider immediately for signs and symptoms of infections including fever, cold symptoms (e.g., rhinorrhea or laryngitis), flu symptoms (e.g., cough, fatigue, body aches), earache or headache, dysuria, oral herpes simplex infection, and painful wounds with erythema and advise patients of the increased risk of infections during and after treatment with RITUXAN [see Warnings and Precautions (5.6)].

Cardiovascular Adverse Reactions

Advise patients of the risk of cardiovascular adverse reactions, including ventricular fibrillation, myocardial infarction, and cardiogenic shock. Advise patients to contact their healthcare provider immediately to report chest pain and irregular heartbeats [see Warnings and Precautions (5.7)].

Renal Toxicity

Advise patients of the risk of renal toxicity. Inform patients of the need for healthcare providers to monitor kidney function [see Warnings and Precautions (5.8)].

Bowel Obstruction and Perforation

Advise patients to contact their healthcare provider immediately for signs and symptoms of bowel obstruction and perforation, including severe abdominal pain or repeated vomiting [see Warnings and Precautions (5.9)].

Embryo-Fetal Toxicity

Advise pregnant women of the potential risk to a fetus. Advise females of reproductive potential to inform their healthcare provider of a known or suspected pregnancy [see Warnings and Precautions (5.11) and Use in Specific Populations (8.1)]

Advise females of reproductive potential to use effective contraception during treatment with RITUXAN and for 12 months after the last dose [see Use in Specific Populations (8.3)].

Lactation

Advise women not to breastfeed during treatment with RITUXAN and for 6 months after the last dose [see Use in Specific Populations (8.2)].

RITUXAN® [rituximab]
Manufactured by:
Genentech, Inc.
A Member of the Roche Group
1 DNA Way
South San Francisco, CA 94080-4990
U.S. License Number: 1048

RITUXAN® is a registered trademark of Biogen.
Jointly marketed by Biogen and Genentech USA, Inc.
©2021 Biogen and Genentech, Inc.

MEDICATION GUIDE
RITUXAN® (ri tuk san)
(rituximab)
injection

What is the most important information I should know about RITUXAN?
RITUXAN can cause serious side effects that can lead to death including:

- Infusion-related reactions. Infusion-related reactions are very common side effects of RITUXAN treatment. Serious infusion-related reactions can happen during your or your child's infusion or within 24 hours after your or your child's infusion of RITUXAN. Your healthcare provider should give you or your child medicines before your or your child's infusion of RITUXAN to decrease your or your child's chance of having a severe infusion-related reaction.
  Tell your healthcare provider or get medical help right away if you or your child get any of these symptoms during or after an infusion of RITUXAN:

- hives (red itchy welts) or rash
- itching
- swelling of your lips, tongue, throat or face
- sudden cough

- shortness of breath, difficulty breathing, or wheezing
- weakness
- dizziness or feel faint
- palpitations (feel like your heart is racing or fluttering)
- chest pain

- Severe skin and mouth reactions. Tell your healthcare provider or get medical help right away if you or your child get any of these symptoms at any time during your treatment with RITUXAN:
  - painful sores or ulcers on your skin, lips or in your mouth
  - blisters
  - peeling skin
  - rash
  - pustules
- Hepatitis B virus (HBV) reactivation. Before you or your child receive RITUXAN treatment, your healthcare provider will do blood tests to check for HBV infection. If you or your child have had hepatitis B or are a carrier of hepatitis B virus, receiving RITUXAN could cause the virus to become an active infection again. Hepatitis B reactivation may cause serious liver problems including liver failure, and death. You or your child should not receive RITUXAN if you or your child have active hepatitis B liver disease. Your healthcare provider will monitor you or your child for hepatitis B infection during and for several months after you or your child stop receiving RITUXAN.
  Tell your healthcare provider right away if you or your child get worsening tiredness, or yellowing of your or your child's skin or white part of your eyes, during treatment with RITUXAN.
- Progressive Multifocal Leukoencephalopathy (PML). PML is a rare, serious brain infection caused by a virus that can happen in people who receive RITUXAN. People with weakened immune systems can get PML. PML can result in death or severe disability. There is no known treatment, prevention, or cure for PML.
  Tell your healthcare provider right away if you or your child have any new or worsening symptoms or if anyone close to you notices these symptoms:

- confusion
- dizziness or loss of balance
- difficulty walking or talking

- decreased strength or weakness on one side of your body
- vision problems

See "What are the possible side effects of RITUXAN?" for more information about side effects.

What is RITUXAN?
RITUXAN is a prescription medicine used to treat:

- Adults with Non-Hodgkin's Lymphoma (NHL): alone or with other chemotherapy medicines.
- Children 6 months of age and older with mature B-cell Non-Hodgkin's Lymphoma (NHL) and mature B-cell acute leukemia (B-AL): in combination with chemotherapy medicines.
- Adults with Chronic Lymphocytic Leukemia (CLL): with the chemotherapy medicines fludarabine and cyclophosphamide.
- Adults with Rheumatoid Arthritis (RA): with another prescription medicine called methotrexate, to reduce the signs and symptoms of moderate to severe active RA in adults, after treatment with at least one other medicine called a Tumor Necrosis Factor (TNF) antagonist has been used and did not work well
- Adults and children 2 years of age and older with Granulomatosis with Polyangiitis (GPA) (Wegener's Granulomatosis) and Microscopic Polyangiitis (MPA): with glucocorticoids, to treat GPA and MPA.
- Adults with Pemphigus Vulgaris (PV): to treat moderate to severe PV.

RITUXAN is not indicated in children less than 2 years of age with GPA or MPA, in children less than 6 months of age with mature B-cell NHL and B-AL, or in children with conditions other than GPA, MPA, B-cell NHL and B-AL.

Before you or your child receive RITUXAN, tell your healthcare provider about all of your or your child's medical conditions, including if you or your child:

- have had a severe reaction to RITUXAN or a rituximab product
- have a history of heart problems, irregular heart beat or chest pain
- have lung or kidney problems
- have an infection or weakened immune system
- have or have had any severe infections including:

- Hepatitis B virus (HBV)
- Hepatitis C virus (HCV)
- Cytomegalovirus (CMV)
- Herpes simplex virus (HSV)

- Parvovirus B19
- Varicella zoster virus (chickenpox or shingles)
- West Nile Virus

- have had a recent vaccination or are scheduled to receive vaccinations. You or your child should not receive certain vaccines before or during treatment with RITUXAN.
- are pregnant or plan to become pregnant. Talk to your healthcare provider about the risks to your or your child's unborn baby if you or your child receive RITUXAN during pregnancy.
  Females who are able to become pregnant:
  - Your healthcare provider should do a pregnancy test to see if you or your child are pregnant before starting RITUXAN.
  - You or your child should use effective birth control (contraception) during treatment with RITUXAN and for 12 months after your or your child's last dose of RITUXAN. Talk to your healthcare provider about effective birth control.
  - Tell your healthcare provider right away if you or your child become pregnant or think that you or your child are pregnant during treatment with RITUXAN.
- are breastfeeding or plan to breastfeed. RITUXAN may pass into your breast milk. Do not breastfeed during treatment and for 6 months after your or your child's last dose of RITUXAN.

Tell your healthcare provider about all the medicines you or your child take, including prescription and over-the-counter medicines, vitamins, and herbal supplements. Especially tell your healthcare provider if you or your child take or have taken:

- a Tumor Necrosis Factor (TNF) inhibitor medicine
- a Disease Modifying Anti-Rheumatic Drug (DMARD)

If you are not sure if your or your child's medicine is one listed above, ask your healthcare provider.

How will I receive RITUXAN?

- RITUXAN is given by infusion through your or your child's central catheter or through a needle placed in a vein (intravenous infusion), in your or your child's arm. Talk to your healthcare provider about how you or your child will receive RITUXAN.
- Your healthcare provider may prescribe medicines before each infusion of RITUXAN to reduce infusion side effects such as fever and chills.
- Your healthcare provider should do blood test regularly to check for side effects to RITUXAN.
- Before each RITUXAN treatment, your healthcare provider or nurse will ask you questions about your or your child's general health. Tell your healthcare provider or nurse about any new symptoms.

What are the possible side effect of RITUXAN?
RITUXAN can cause serious side effects, including:

- See "What is the most important information I should know about RITUXAN?"
- Tumor Lysis Syndrome (TLS). TLS is caused by the fast breakdown of cancer cells. TLS can cause you or your child to have:
  - kidney failure and the need for dialysis treatment
  - abnormal heart rhythm
  TLS can happen within 12 to 24 hours after an infusion of RITUXAN. Your healthcare provider may do blood tests to check you or your child for TLS. Your healthcare provider may give you or your child medicine to help prevent TLS.
  Tell your healthcare provider right away if you or your child have any of the following signs or symptoms or TLS:

- nausea
- vomiting

- diarrhea
- lack of energy

- Serious infections. Serious infections can happen during and after treatment with RITUXAN, and can lead to death. RITUXAN can increase your or your child's risk of getting infections and can lower the ability of your or your child's immune system to fight infections. Types of serious infections that can happen with RITUXAN include bacterial, fungal, and viral infections. After receiving RITUXAN, some people have developed low levels of certain antibodies in their blood for a long period of time (longer than 11 months). Some of these people with low antibody levels developed infections. People with serious infections should not receive RITUXAN. Tell your healthcare provider right away if you or your child have any symptoms of infection:
  - fever
  - cold symptoms, such as runny nose or sore throat that do not go away
  - flu symptoms, such as cough, tiredness, and body aches
  - earache or headache
  - pain during urination
  - cold sores in the mouth or throat
  - cuts, scrapes or incisions that are red, warm, swollen or painful
- Heart problems. RITUXAN may cause chest pain, irregular heartbeats, and heart attack. Your healthcare provider may monitor your or your child's heart during and after treatment with RITUXAN if you or your child have symptoms or heart problems or have a history of heart problems. Tell your healthcare provider right away if you or your child have chest pain or irregular heartbeats during treatment with RITUXAN.
- Kidney problems, especially if you or your child are receiving RITUXAN for NHL. RITUXAN can cause severe kidney problems that lead to death. Your healthcare provider should do blood tests to check how well your or your child's kidneys are working.
- Stomach and Serious bowel problems that can sometimes lead to death. Bowel problems, including blockage or tears in the bowel can happen if you or your child receive RITUXAN with chemotherapy medicines. Tell your healthcare provider right away if you or your child have any severe stomach-area (abdomen) pain or repeated vomiting during treatment with RITUXAN.

Your healthcare provider will stop treatment with RITUXAN if you have severe, serious or life-threatening side effects.
The most common side effects of RITUXAN include:

- infusion-related reactions (see "What is the most important information I should know about RITUXAN?")
- infections (may include fever, chills)
- body aches
- tiredness
- nausea

In adults with GPA or MPA the most common side effects of RITUXAN also include:

- low white and red blood cells
- swelling
- diarrhea
- muscle spasms

In children with B-cell NHL or B-AL who receive RITUXAN with chemotherapy, the most common side effects include:

- decreased white blood cells with fever
- mouth sores
- inflammation of the upper intestine
- serious infection throughout the body and organs (sepsis)
- changes in liver function blood tests
- low level of potassium in the blood

Other side effects with RITUXAN include:

- aching joints during or within hours of receiving an infusion
- more frequent upper respiratory tract infection

These are not all of the possible side effects with RITUXAN.
Call your doctor for medical advice about side effects. You may report side effects to FDA at 1-800-FDA-1088

General information about the safe and effective use of RITUXAN.
Medicines are sometimes prescribed for purposes other than those listed in a Medication Guide. You can ask your pharmacist or healthcare provider for information about RITUXAN that is written for healthcare providers.

What are the ingredients in RITUXAN?
Active ingredient: rituximab
Inactive ingredients: polysorbate 80, sodium chloride, sodium citrate dihydrate, and water for injection, USP.
Manufactured by: Genentech, Inc., A Member of the Roche Group, 1 DNA Way, South San Francisco, CA 94080-4990
Jointly Marketed by Biogen and Genentech USA, Inc.
U.S. License Number: 1048
RITUXAN® is a registered trademark of Biogen. ©2021 Biogen and Genentech, Inc.
For more information, go to www.RITUXAN.com or call 1-877-436-3683.

This Medication Guide has been approved by the U.S. Food and Drug Administration.

Revised: 04/2024

Representative sample of labeling (see the HOW SUPPLIED section for complete listing):

PRINCIPAL DISPLAY PANEL - 100 mg Vial Carton

NDC 50242-051-21

Rituxan®

(rituximab)

Injection

100 mg/10 mL (10 mg/mL)

For Intravenous Use

100 mg
Rx only
One 100 mg vial

Jointly Marketed by:
Biogen and Genentech USA, Inc.

10223019

PRINCIPAL DISPLAY PANEL - 500 mg Vial Carton

NDC 50242-053-06

Rituxan®

(rituximab)

Injection

500 mg/50 mL (10 mg/mL)

For Intravenous Use

500 mg

Rx only
One 500 mg vial

Jointly Marketed by:
Biogen and Genentech USA, Inc.

10223022